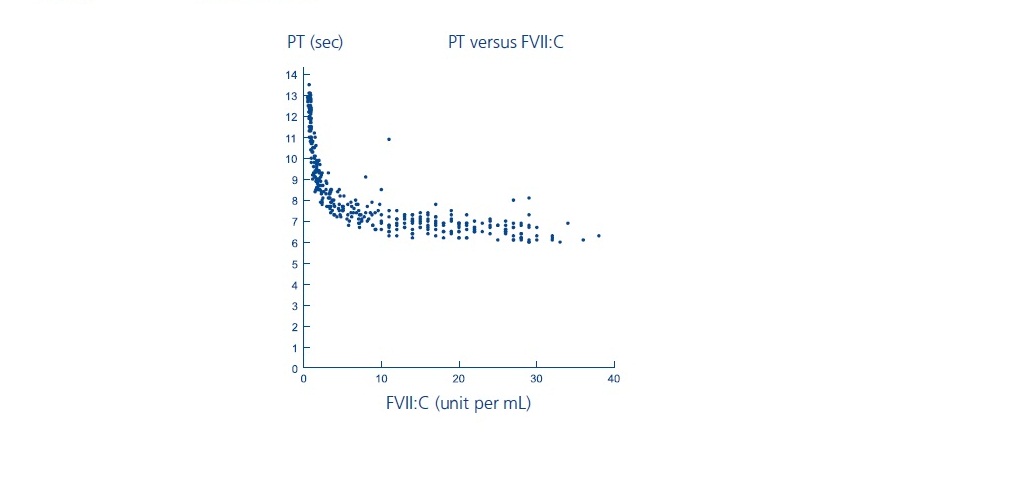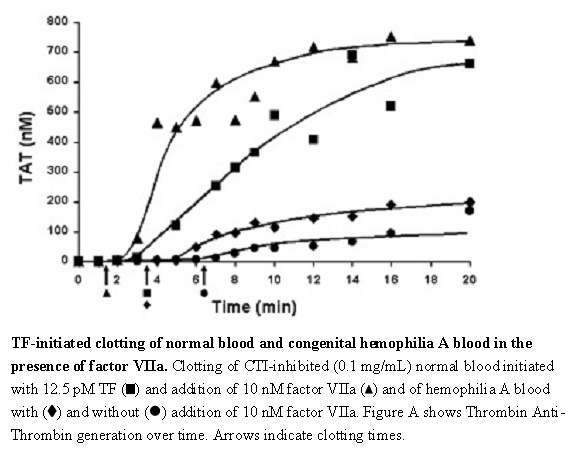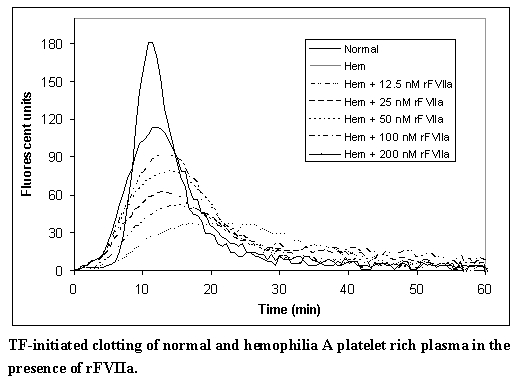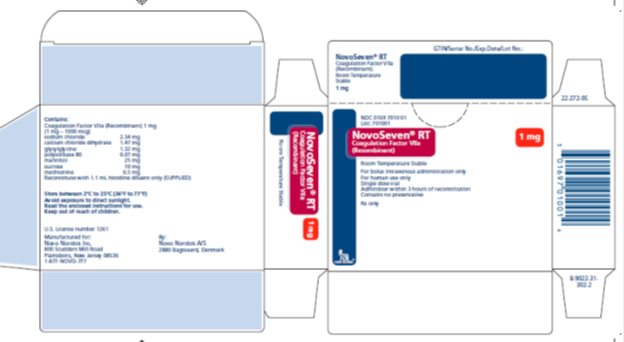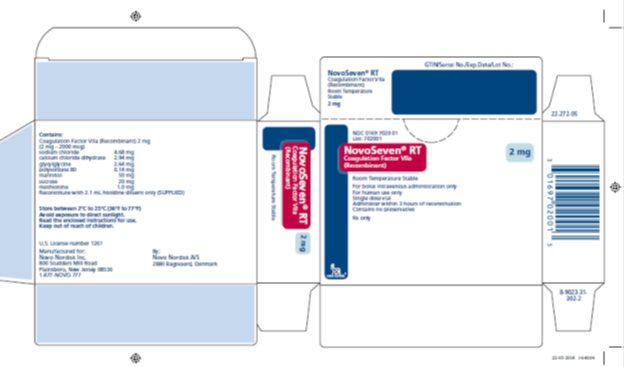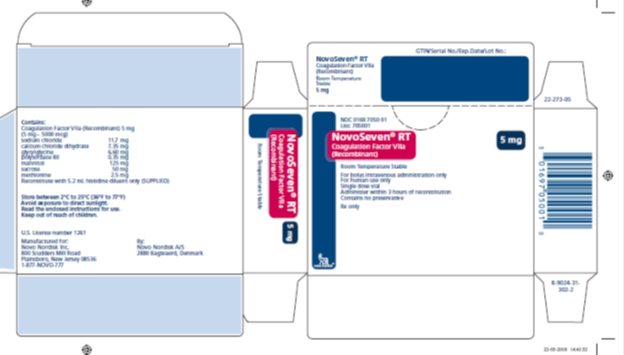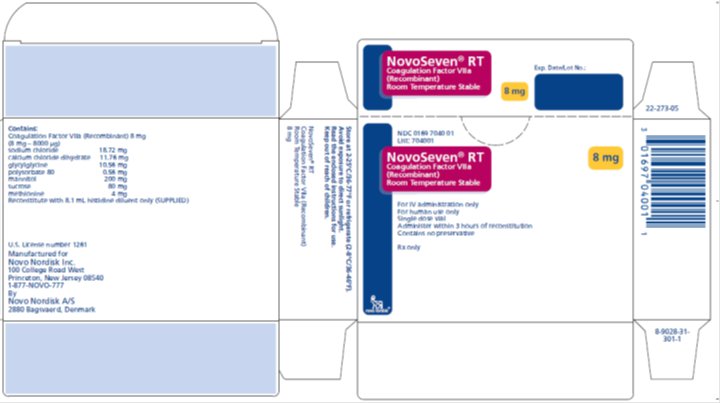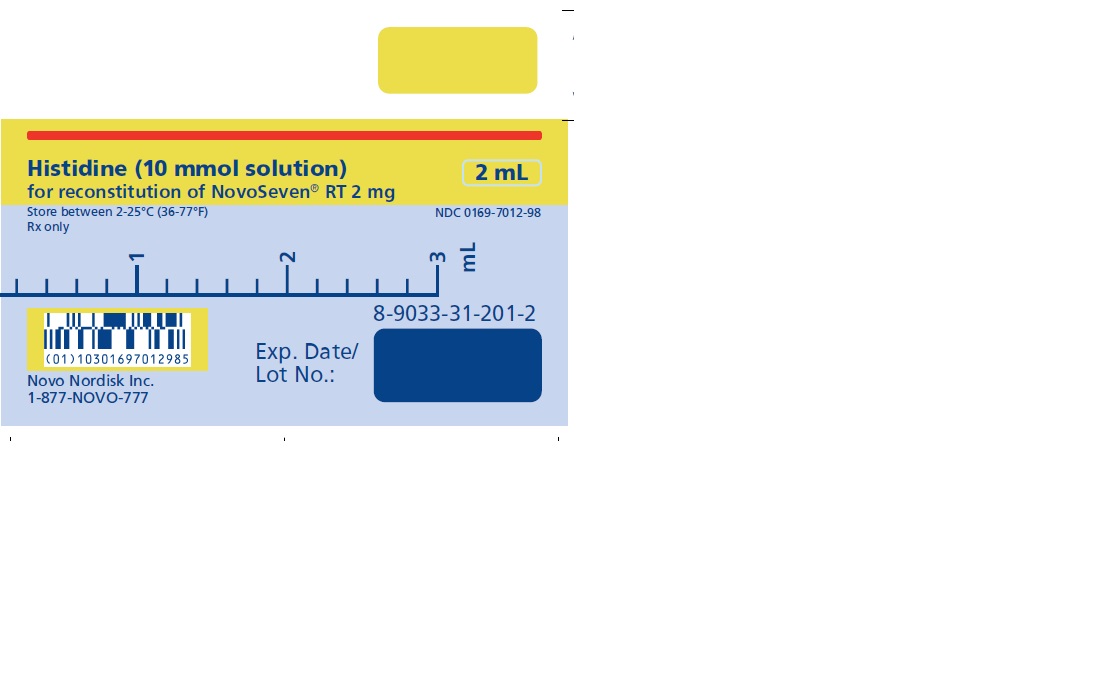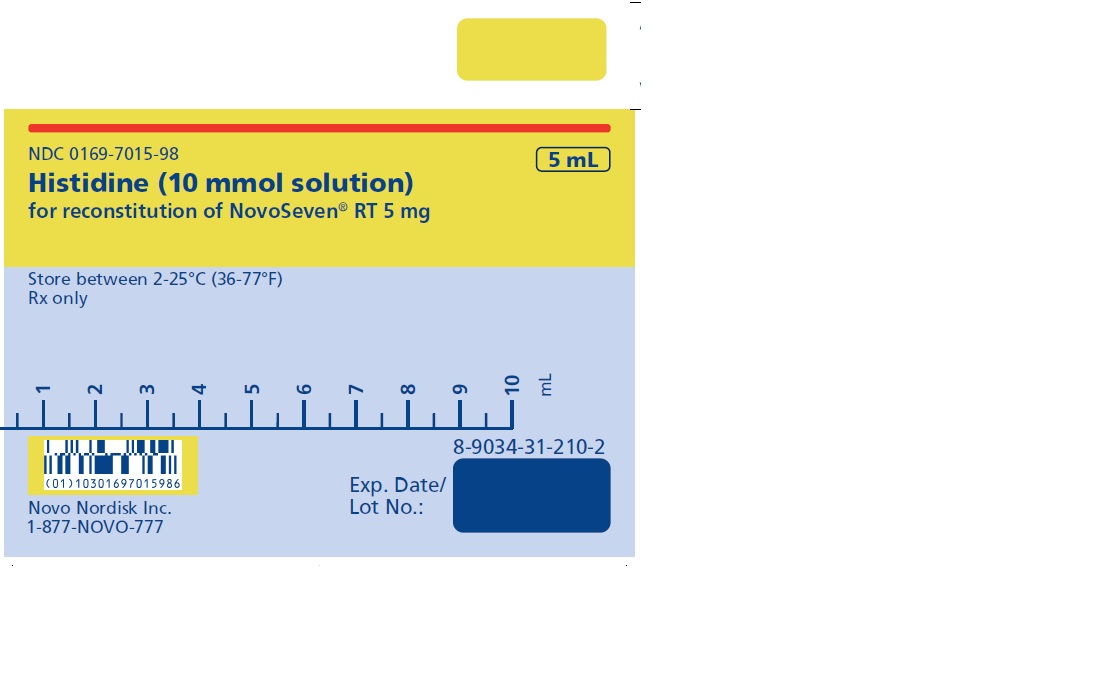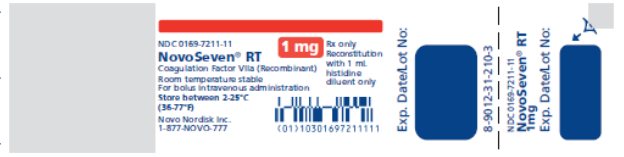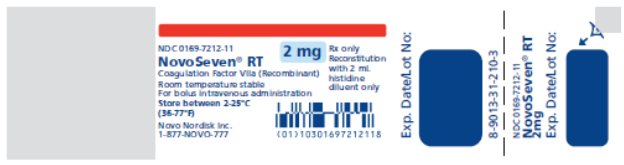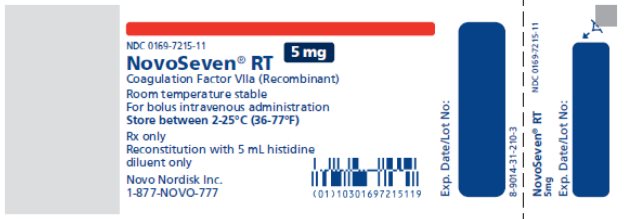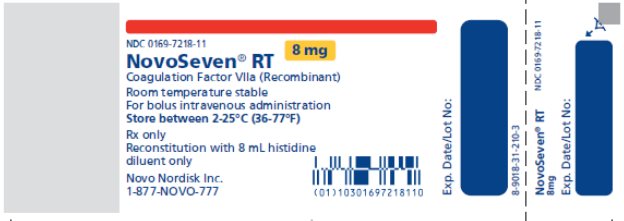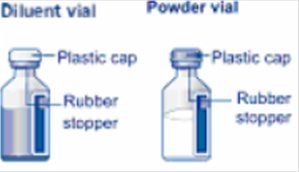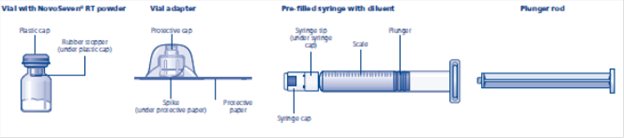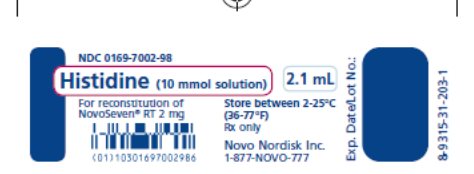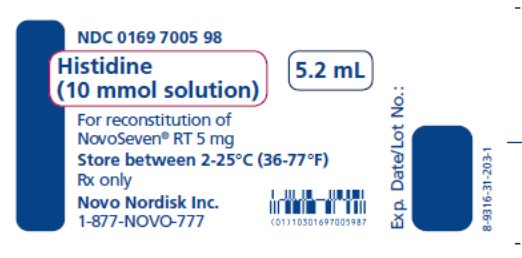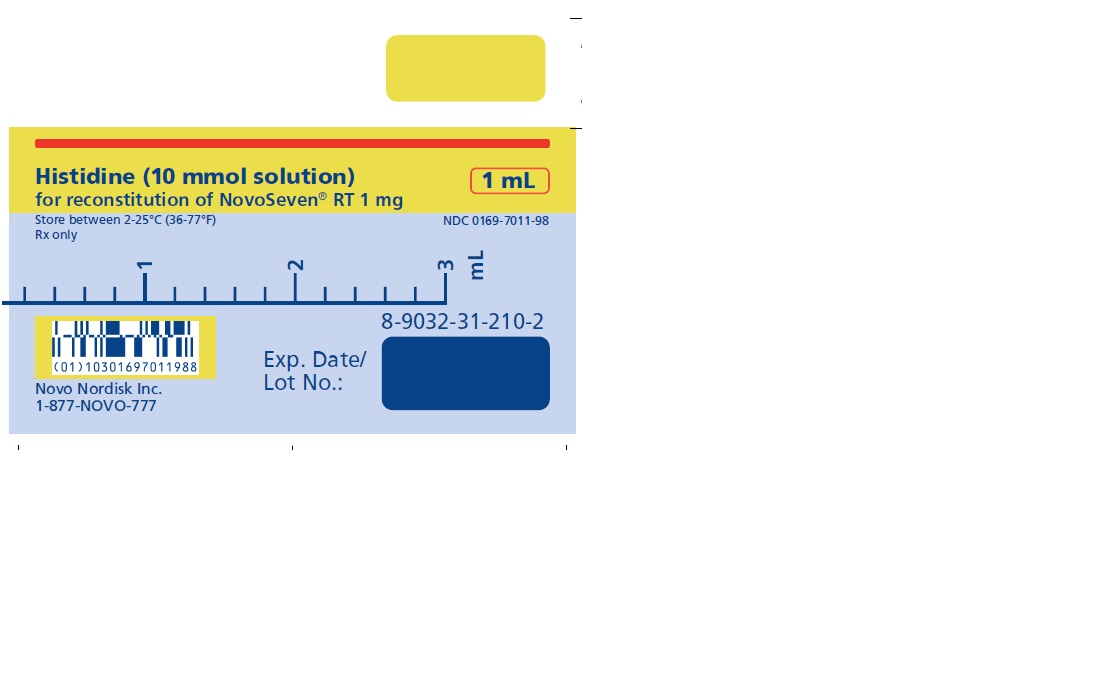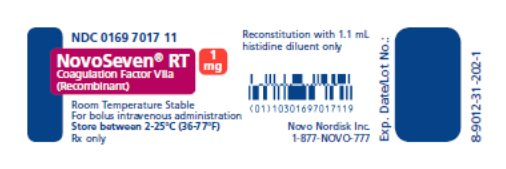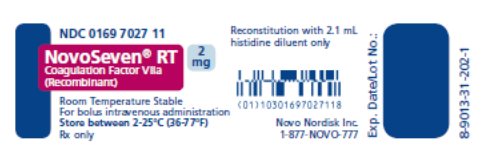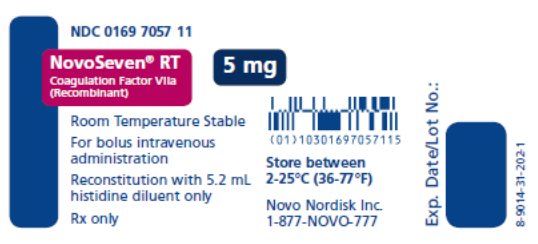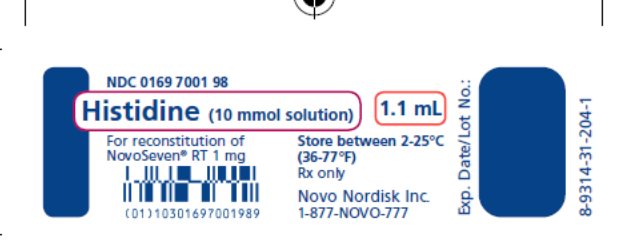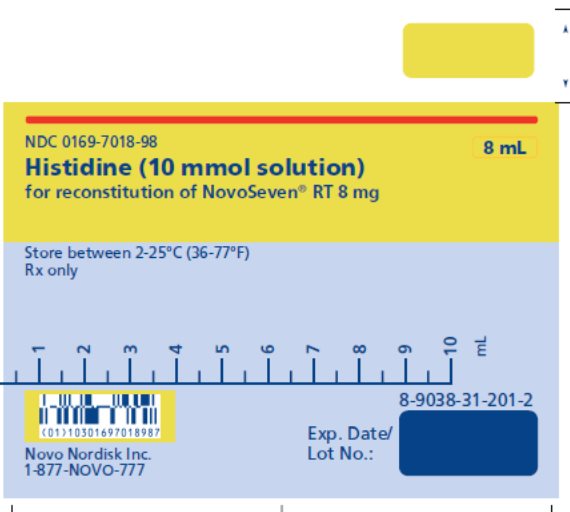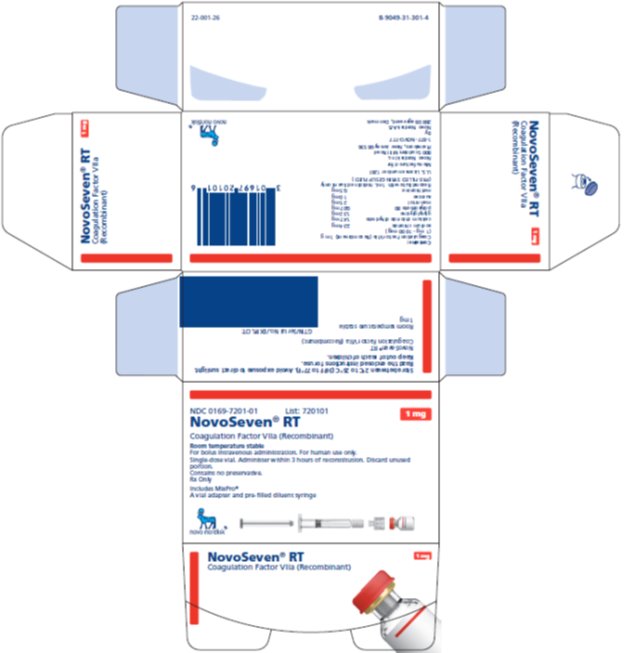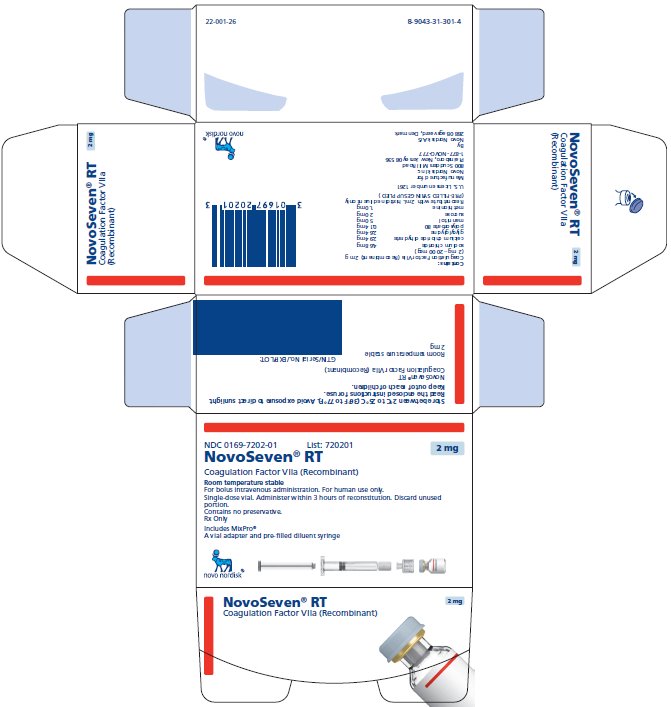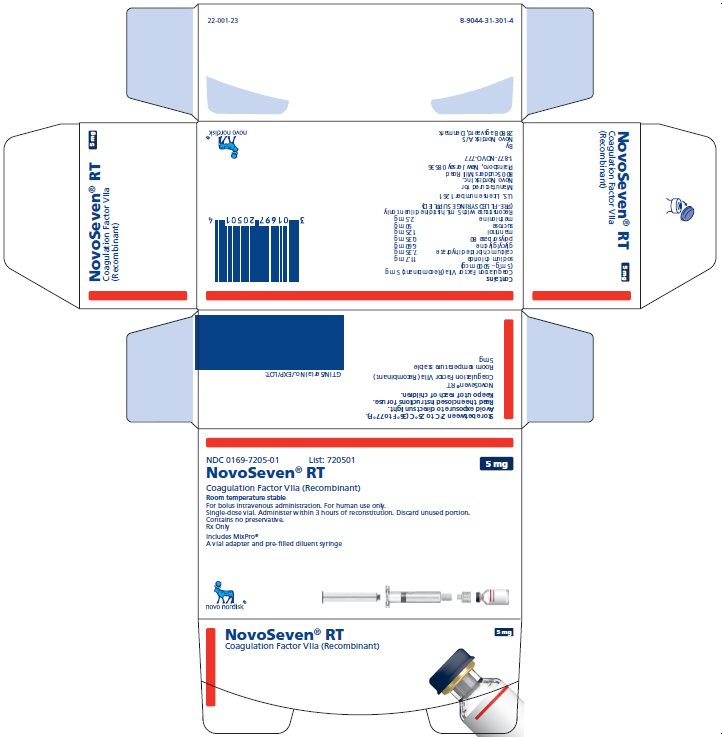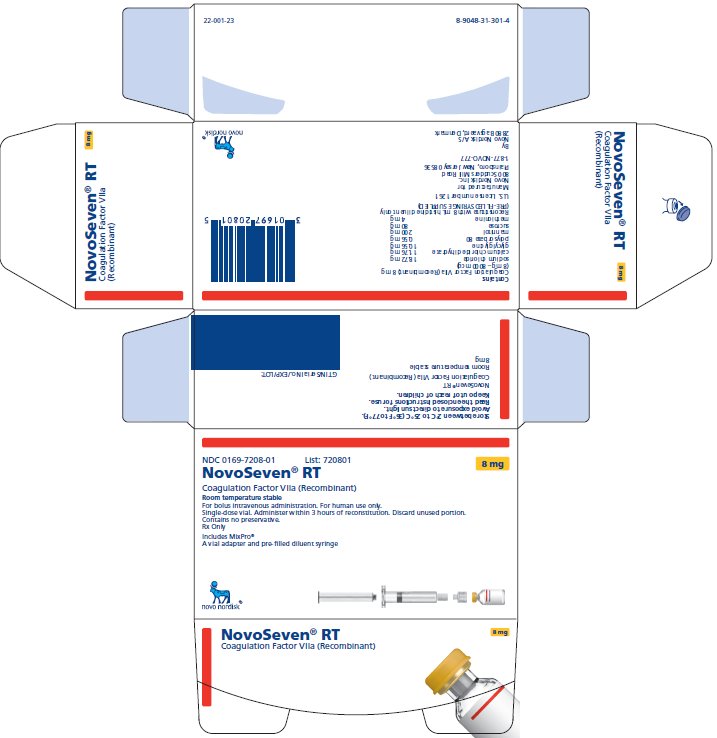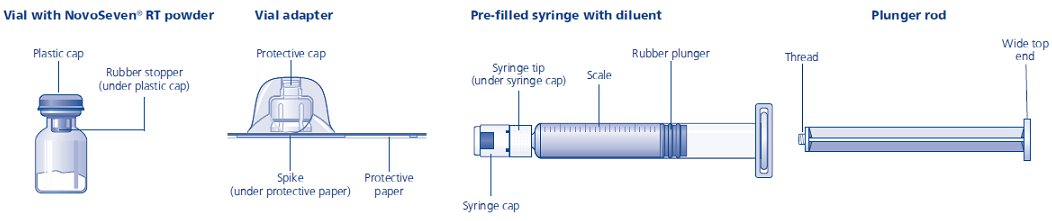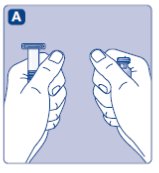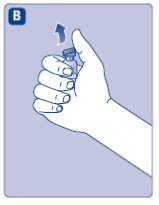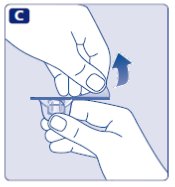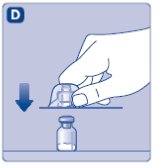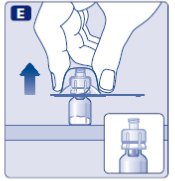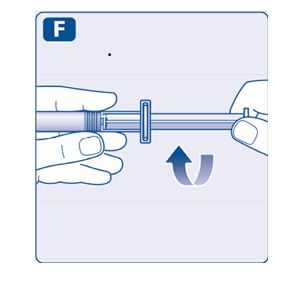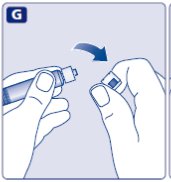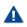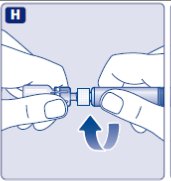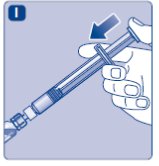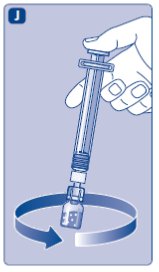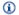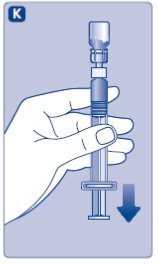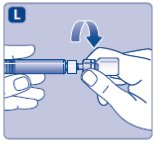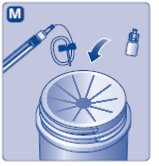 DRUG LABEL: NovoSeven
NDC: 0169-7010 | Form: KIT | Route: INTRAVENOUS
Manufacturer: Novo Nordisk
Category: other | Type: PLASMA DERIVATIVE
Date: 20200710

ACTIVE INGREDIENTS: COAGULATION FACTOR VIIA RECOMBINANT HUMAN 1 mg/1 mL
INACTIVE INGREDIENTS: CALCIUM CHLORIDE 1.5 mg/1 mL; DIGLYCINE 1.3 mg/1 mL; MANNITOL 25 mg/1 mL; METHIONINE 0.5 mg/1 mL; POLYSORBATE 80 0.1 mg/1 mL; SODIUM CHLORIDE 2.3 mg/1 mL; SUCROSE 10 mg/1 mL; HISTIDINE 1.6 mg/1 mL; WATER

HIGHLIGHTS OF PRESCRIBING INFORMATION

These highlights do not include all the information needed to use NOVOSEVEN RT safely and effectively. See full prescribing information for NOVOSEVEN RT.
NOVOSEVEN RT (coagulation Factor VIIa, recombinant)
lyophilized powder for solution, for intravenous use
Initial U.S. Approval: 1999

WARNING: THROMBOSIS

See full prescribing information for complete boxed warning

- Serious arterial and venous thrombotic events following administration of NOVOSEVEN RT have been reported. (5.1)
- Discuss the risks and explain the signs and symptoms of thrombotic and thromboembolic events to patients who will receive NOVOSEVEN RT
- Monitor patients for signs or symptoms of activation of the coagulation system and for thrombosis. (5.1)

1 INDICATIONS AND USAGE

NOVOSEVEN RT, Coagulation Factor VIIa (Recombinant) is indicated for:

- Treatment of bleeding episodes and perioperative management in adults and children with hemophilia A or B with inhibitors, congenital Factor VII (FVII) deficiency, and Glanzmann’s thrombasthenia with refractoriness to platelet transfusions, with or without antibodies to platelets (1)
- Treatment of bleeding episodes and perioperative management in adults with acquired hemophilia (1)

2 DOSAGE AND ADMINISTRATION

For intravenous injection only

Bleeding Episodes (2.1)

Indication | Dosing Recommendation
Congenital Hemophilia A or B with Inhibitors | - 90 mcg/kg every 2 hours, adjustable based on severity of bleeding until hemostasis is achieved - 90 mcg/kg every 3-6 hours after hemostasis is achieved for severe bleeds
Acquired Hemophilia | - 70-90 mcg/kg every 2-3 hours until hemostasis is achieved
Congenital Factor VII Deficiency | - 15-30 mcg/kg every 4-6 hours until hemostasis is achieved
Glanzmann’s Thrombasthenia | - 90 mcg/kg every 2-6 hours until hemostasis is achieved

Peri-operative Management (2.1)

Indication | Dosing Recommendation
Congenital Hemophilia A or B with Inhibitors | Minor:; - 90 mcg/kg immediately before surgery, repeat every 2 hours during surgery - 90 mcg/kg every 2 hours after surgery for 48 hours, then every 2-6 hours until healing has occurred; Major:; - 90 mcg/kg immediately before surgery, repeat every 2 hours during surgery - 90 mcg/kg every 2 hours after surgery for 5 days, then every 4 hours or by continuous infusion at 50 mcg/kg/hr until healing has occurred
Acquired Hemophilia | - 70-90 mcg/kg immediately before surgery and every 2-3 hours for the duration of surgery and until hemostasis is achieved
Congenital Factor VII Deficiency | - 15-30 mcg/kg immediately before surgery and every 4-6 hours for the duration of surgery and until hemostasis is achieved
Glanzmann’s Thrombasthenia | - 90 mcg/kg immediately before surgery and repeat every 2 hours for the duration of the procedure - 90 mcg/kg every 2-6 hours to prevent post-operative bleeding

3 DOSAGE FORMS AND STRENGTHS

Available as lyophilized powder in single-dose vials of 1, 2, 5, or 8 mg recombinant coagulation factor VIIa (FVIIa). After reconstitution with specified volume of histidine diluent, the final solution contains 1 mg per mL (1000 micrograms per mL) of recombinant FVIIa (3)

4 CONTRAINDICATIONS

None known (4)

5 WARNINGS AND PRECAUTIONS

- Hypersensitivity reactions, including anaphylaxis, can occur with NOVOSEVEN RT. Discontinue infusion and administer appropriate treatment if symptoms appear (5.2)
- Antibody to FVII may occur in FVII deficient patients. Monitor Factor VII deficient patients for prothrombin time (PT) and FVII coagulant activity, and for antibody formation to NOVOSEVEN RT (5.3)

6 ADVERSE REACTIONS

The most common and serious adverse reactions in clinical trials are thrombotic events. Thrombotic adverse reactions following the administration of NOVOSEVEN in clinical trials occurred in 4% of patients with acquired hemophilia and 0.2% of bleeding episodes in patients with congenital hemophilia (6)

To report SUSPECTED ADVERSE REACTIONS, contact Novo Nordisk Inc. at 1-877-668-6777 or FDA at 1-800-FDA-1088 or www.fda.gov/medwatch.

7 DRUG INTERACTIONS

- Avoid simultaneous use of NOVOSEVEN RT and aPCCs (activated prothrombin complex concentrates) (7)
- Do not administer NOVOSEVEN RT with coagulation factor XIII (FXIII) (7)

FULL PRESCRIBING INFORMATION

WARNING: THROMBOSIS

- Serious arterial and venous thrombotic events following administration of NOVOSEVEN RT have been reported. [See Warnings and Precautions (5.1)]
- Discuss the risks and explain the signs and symptoms of thrombotic and thromboembolic events to patients who will receive NOVOSEVEN RT. [See Warnings and Precautions (5.1)]
- Monitor patients for signs or symptoms of activation of the coagulation system and for thrombosis. [See Warnings and Precautions (5.1)]

1 INDICATIONS AND USAGE

NOVOSEVEN RT, Coagulation Factor VIIa (Recombinant), is indicated for:

- Treatment of bleeding episodes and peri-operative management in adults and children with hemophilia A or B with inhibitors, congenital Factor VII (FVII) deficiency, and Glanzmann’s thrombasthenia with refractoriness to platelet transfusions, with or without antibodies to platelets.
- Treatment of bleeding episodes and peri-operative management in adults with acquired hemophilia.

2 DOSAGE AND ADMINISTRATION

For intravenous administration only

2.1 Dose

- Use hemostasis evaluation to determine the effectiveness of NOVOSEVEN RT and to provide a basis for modification of the NOVOSEVEN RT treatment schedule.
- Coagulation parameters do not necessarily correlate with or predict the effectiveness of NOVOSEVEN RT.

Treatment of Acute Bleeding Episodes

NOVOSEVEN RT dosing for the treatment of acute bleeding episodes is provided in Table 1.

Table 1: Dosing for Treatment of Acute Bleeding Episodes

Dose [The minimum effective dose has not been determined] and Frequency | Duration of Therapy | Additional Information
Congenital Hemophilia A or B with Inhibitors
Hemostatic; 90 mcg/kg every two hours, adjustable based on severity of bleeding; Post-Hemostatic; 90 mcg/kg every 3-6 hours for severe bleeds | Until hemostasis is achieved, or until the treatment has been judged to be inadequate; After hemostasis is achieved to maintain the hemostatic plug | The appropriate duration of post-hemostatic dosing has not been studied
Acquired Hemophilia
70-90 mcg/kg every 2-3 hours | Until hemostasis is achieved
Congenital Factor VII Deficiency
15-30 mcg/kg every 4-6 hours | Until hemostasis is achieved | Effective treatment has been achieved with doses as low as 10 micrograms per kg body weight.; Adjust dose and frequency of injections to each individual patient
Glanzmann’s Thrombasthenia
90 mcg/kg every 2-6 hours | In severe bleeding episodes requiring systemic hemostatic therapy until hemostasis is achieved | Platelet transfusions are the primary treatment in patients with Glanzmann’s Thrombasthenia without refractoriness to platelets or in patients without platelet-specific antibodies

Congenital Hemophilia A or B with inhibitors

- Dose and administration interval may be adjusted to the individual patient based on the severity of the bleeding.^1
- For patients treated for joint or muscle bleeds, a decision on outcome was reached for a majority of patients within eight doses although more doses were required for severe bleeds. A majority of patients who reported adverse experiences received more than twelve doses. Monitor and minimize the duration of any post-hemostatic dosing.

Perioperative Management

NOVOSEVEN RT dosing for prevention of bleeding in surgical interventions or invasive procedures (perioperative management) is provided in Table 2.

Table 2: Dosing for Perioperative Management

Type of Surgery | Dose and Frequency | Additional Information
Congenital Hemophilia A or B with Inhibitors
Minor | Initial: 90 mcg/kg immediately before surgery and repeat every 2 hours for the duration of the surgery; Post surgical:; 90 mcg/kg every 2 hours for 48 hours then every 2-6 hours until healing occurs
Major | Initial:; 90 mcg/kg immediately before surgery and repeat every 2 hours for the duration of the surgery; Post surgical:; 90 mcg/kg every 2 hours for 5 days then every 4 hours or by continuous infusion at 50 mcg/kg/hr until healing occurs | Additional bolus doses can be given
Acquired Hemophilia
Minor or Major | 70-90 mcg/kg immediately before surgery and repeat every 2-3 hours for the duration of the surgery and until hemostasis is achieved [The minimum effective dose has not been determined.]
Congenital Factor VII Deficiency
Minor or Major | 15-30 mcg/kg immediately before surgery and repeat every 4-6 hours for the duration of the surgery and until hemostasis is achieved*; Adjust dose and frequency of injections to each individual patient | Doses as low as 10 micrograms per kg body weight can be effective
Glanzmann’s Thrombasthenia
Minor or Major | Initial:; 90 mcg/kg immediately before surgery and repeat every 2 hours for the duration of the procedure; Post surgical:; 90 mcg/kg every 2-6 hours to prevent post-operative bleeding | Higher doses of 100-140 micrograms per kg can be used for surgical patients who have clinical refractoriness with or without platelet-specific antibodies

2.2 Reconstitution

- Follow the procedures below for the preparation and reconstitution of NOVOSEVEN RT. For questions regarding reconstitution, please contact Novo Nordisk at 1-877-NOVO-777.
- Calculate the NOVOSEVEN RT dosage and select the appropriate NOVOSEVEN RT package provided with either 1 histidine diluent vial or 1 pre-filled histidine diluent syringe.
- Reconstitute only with the histidine diluent provided with NOVOSEVEN RT.

NOVOSEVEN RT package containing 1 vial of NOVOSEVEN RT powder and 1 vial of histidine diluent:

1. Always use aseptic technique.
2. Bring NOVOSEVEN RT (white, lyophilized powder) and the specified volume of histidine (diluent) to room temperature, but not above 37°C (98.6° F). The specified volume of diluent corresponding to the amount of NOVOSEVEN RT is as follows:
  1 mg (1000 micrograms) vial + 1.1 mL Histidine diluent
  2 mg (2000 micrograms) vial + 2.1 mL Histidine diluent
  5 mg (5000 micrograms) vial + 5.2 mL Histidine diluent
  8 mg (8000 micrograms) vial + 8.1 mL Histidine diluent
3. Remove caps from the NOVOSEVEN RT vials to expose the central portion of the rubber stopper. Cleanse the rubber stoppers with an alcohol swab and allow to dry prior to use.
4. Draw back the plunger of a sterile syringe (attached to sterile needle) and admit air into the syringe. It is recommended to use syringe needles of gauge size 20-26.
5. Insert the needle of the syringe into the Histidine diluent vial. Inject air into the vial and withdraw the quantity required for reconstitution.
6. Insert the syringe needle containing the diluent into the NOVOSEVEN RT vial through the center of the rubber stopper, aiming the needle against the side so that the stream of liquid runs down the vial wall (the NOVOSEVEN RT vial does not contain a vacuum). Do not inject the diluent directly on the NOVOSEVEN RT powder.
7. Gently swirl the vial until all the material is dissolved. The reconstituted solution is a clear, colorless solution which may be stored either at room temperature or refrigerated for up to 3 hours after reconstitution. After reconstitution with the specified volume of diluent, each vial contains approximately 1 mg per mL NOVOSEVEN RT (1000 micrograms per mL).

NOVOSEVEN RT package containing 1 vial of NOVOSEVEN RT powder and 1 pre-filled histidine diluent syringe with vial adapter for needleless reconstitution:

1. Always use aseptic technique.
2. Bring NOVOSEVEN RT (white, lyophilized powder) and the specified volume of histidine (diluent) to room temperature, but not above 37°C (98.6° F). The specified volume of diluent corresponding to the amount of NOVOSEVEN RT is as follows:
  1 mg (1000 micrograms) vial + 1 mL Histidine diluent in pre-filled syringe
  2 mg (2000 micrograms) vial + 2 mL Histidine diluent in pre-filled syringe
  5 mg (5000 micrograms) vial + 5 mL Histidine diluent in pre-filled syringe
  8 mg (8000 micrograms) vial + 8 mL Histidine diluent in pre-filled syringe
3. Remove cap from the NOVOSEVEN RT vial. Cleanse the rubber stopper with an alcohol swab and allow to dry prior to use.
4. Peel back the protective paper from the vial adapter. Do not remove the vial adapter from the package.
5. Place the NOVOSEVEN RT vial on a flat surface. While holding the vial adapter package, place the vial adapter over the NOVOSEVEN RT vial and press down firmly on the package until the vial adapter spike penetrates the rubber stopper.
6. Attach the plunger rod to the syringe. Turn the plunger rod clockwise into the plunger inside the pre-filled diluent syringe until resistance is felt. Remove the syringe cap from the pre-filled diluent syringe and screw onto the vial adapter.
7. Push the plunger rod to slowly inject all the diluent into the vial. Keep the plunger rod pressed down and swirl the vial gently until the powder is dissolved. The reconstituted solution is a clear, colorless solution which may be stored fully assembled either at room temperature or refrigerated for up to 3 hours after reconstitution. After reconstitution with the specified volume of diluent, each vial contains approximately 1 mg per mL NOVOSEVEN RT (1000 micrograms per mL).

2.3 Administration

For intravenous injection only

- Inspect the reconstituted NOVOSEVEN RT visually for particulate matter and discoloration prior to administration, whenever solution and container permit. Do not use if particulate matter or discoloration is observed.
- Do not freeze reconstituted NOVOSEVEN RT or store it in syringes.
- Administer within 3 hours after reconstitution.
- Do not mix with other infusion solutions.
- Discard any unused solution.

Perform the following procedures immediately prior to administration:

NOVOSEVEN RT package containing 1 vial of NOVOSEVEN RT powder and 1 vial of histidine diluent:

1. Always use aseptic technique.
2. Draw back the plunger of a sterile syringe (attached to sterile needle) and admit air into the syringe.
3. Insert needle into the vial of reconstituted NOVOSEVEN RT. Inject air into the vial and then withdraw
the appropriate amount of reconstituted NOVOSEVEN RT into the syringe.
4. Remove and discard the needle from the syringe.

NOVOSEVEN RT package containing 1 vial of NOVOSEVEN RT powder and 1 pre-filled histidine diluent syringe with vial adapter for needleless reconstitution:

1. Always use aseptic technique.
  2. Invert the NOVOSEVEN RT vial. Stop pushing the plunger rod and let it move back on its own while
the mixed solution fills the syringe. Pull the plunger rod slightly downwards to draw the mixed solution into the syringe. Tap the syringe to remove air bubbles and withdraw the required dose amount of reconstituted NOVOSEVEN RT into the syringe.
3. Unscrew the vial adapter with the vial. Discard the empty NOVOSEVEN RT vial with the vial adapter
attached.

Caution:

- The pre-filled diluent syringe is made of glass with an internal tip diameter of 0.037 inches, and is compatible with a standard Luer-lock connector.
- Some needleless connectors for intravenous catheters are incompatible with the glass diluent syringes (for example, certain connectors with an internal spike, such as Clave® /MicroClave®, InVision-Plus®, InVision-Plus CS®, InVision-Plus® Junior®, Bionector®), and their use can damage the connector and affect administration. To administer product through incompatible needleless connectors, withdraw reconstituted product into a standard 10 mL sterile Luer-lock plastic syringe.
- If you have encountered any problems with attaching the pre-filled histidine diluent syringe to any Luer lock compatible device, please contact Novo Nordisk at (877) 668-6777.

Administer NOVOSEVEN RT bolus infusion using the following procedures:

1. Administer as a slow bolus injection over 2 to 5 minutes, depending on the dose administered.
2. If line needs to be flushed before or after NOVOSEVEN RT administration, use 0.9% Sodium Chloride
Injection, USP.
3. Discard any unused reconstituted NOVOSEVEN RT after 3 hours.

Administer NOVOSEVEN RT continuous infusion for perioperative management using the following procedures:

1. Administer as a continuous infusion at 50 mcg/kg/hr using an infusion pump.
2. If line needs to be flushed before or after NOVOSEVEN RT administration, use 0.9% Sodium Chloride Injection, USP.

3 DOSAGE FORMS AND STRENGTHS

NOVOSEVEN RT is available as a white lyophilized powder in single-dose vials containing 1 mg (1000 micrograms), 2 mg (2000 micrograms), 5 mg (5000 micrograms), or 8 mg (8000 micrograms) recombinant coagulation Factor VIIa (rFVIIa) per vial.

The diluent for reconstitution of NOVOSEVEN RT is a 10 mmol solution of L-histidine in water for injection. It is a clear colorless solution provided in a vial or a pre-filled diluent syringe and is referred to as the histidine diluent.

After reconstitution with the histidine diluent, the final solution contains approximately 1 mg per mL NOVOSEVEN RT (1000 micrograms per mL).

4 CONTRAINDICATIONS

None known.

5 WARNINGS AND PRECAUTIONS

5.1 Thrombosis

- Serious arterial and venous thrombotic events have been reported in clinical trials and postmarketing surveillance.
- Patients with congenital hemophilia receiving concomitant treatment with aPCCs (activated prothrombin complex concentrates), older patients particularly with acquired hemophilia and receiving other hemostatic agents, or patients with a history of cardiac, vascular disease or predisposed to thrombotic events may have an increased risk of developing thrombotic events [See Adverse Reactions (6.1) and Drug Interactions (7)].
- Monitor patients who receive NOVOSEVEN RT for development of signs or symptoms of activation of the coagulation system or thrombosis. When there is laboratory confirmation of intravascular coagulation or presence of clinical thrombosis, reduce the dose of NOVOSEVEN RT or stop the treatment, depending on the patient's condition.

5.2 Hypersensitivity Reactions

Hypersensitivity reactions, including anaphylaxis, can occur with NOVOSEVEN RT. Patients with a known hypersensitivity to mouse, hamster, or bovine proteins may be at a higher risk of hypersensitivity reactions. Discontinue infusion and administer appropriate treatment when hypersensitivity reactions occur.

5.3 Antibody Formation in Factor VII Deficient Patients

Factor VII deficient patients should be monitored for prothrombin time (PT) and factor VII coagulant activity before and after administration of NOVOSEVEN RT. If the factor VIIa activity fails to reach the expected level, or prothrombin time is not corrected, or bleeding is not controlled after treatment with the recommended doses, antibody formation may be suspected and analysis for antibodies should be performed.

5.4 Laboratory Tests

Laboratory coagulation parameters (PT/INR, aPTT, FVII:C) have shown no direct correlation to achieving hemostasis. Assays of prothrombin time (PT/INR), activated partial thromboplastin time (aPTT), and plasma FVII clotting activity (FVII:C), may give different results with different reagents. Treatment with NOVOSEVEN has been shown to produce the following characteristics:

PT: As shown below, in patients with hemophilia A/B with inhibitors, the PT shortened to about a 7-second plateau at a FVII:C level of approximately 5 units per mL. For FVII:C levels > 5 units per mL, there is no further change in PT. The clinical relevance of prothrombin time shortening following NOVOSEVEN RT administration is unknown.

INR: NOVOSEVEN has demonstrated the ability to normalize INR. However, INR values have not been shown to directly predict bleeding outcomes, nor has it been possible to demonstrate the impact of NOVOSEVEN on bleeding times/volume in models of clinically-induced bleeding in healthy volunteers who had received Warfarin, when laboratory parameters (PT/INR, aPTT, thromboelastogram) have normalized.
aPTT: While administration of NOVOSEVEN shortens the prolonged aPTT in hemophilia A/B patients with inhibitors, normalization has usually not been observed in doses shown to induce clinical improvement. Data indicate that clinical improvement was associated with a shortening of aPTT of 15 to 20 seconds.

FVIIa:C: FVIIa:C levels were measured two hours after NOVOSEVEN administration of 35 micrograms per kg body weight and 90 micrograms per kg body weight following two days of dosing at two hour intervals. Average steady state levels were 11 and 28 units per mL for the two dose levels, respectively.

6 ADVERSE REACTIONS

The most common and serious adverse reactions in clinical trials are thrombotic events. Thrombotic adverse reactions following the administration of NOVOSEVEN in clinical trials occurred in 4% of patients with acquired hemophilia and 0.2% of bleeding episodes in patients with congenital hemophilia.

6.1 Clinical Trials Experience

Because clinical studies are conducted under widely varying conditions, adverse reaction rates observed in the clinical trials of a drug product cannot be directly compared to rates in clinical trials of another drug, and may not reflect rates observed in practice.

Adverse reactions outlined below have been reported from clinical trials and data collected in registries.

Hemophilia A or B Patients with Inhibitors

In two studies for hemophilia A or B patients with inhibitors treated for bleeding episodes (N=298), adverse reactions were reported in ≥2% of the patients that were treated with NOVOSEVEN for 1,939 bleeding episodes (see Table 3 below).

Table 3: Adverse Reactions Reported in ≥2% of the 298 Patients with Hemophilia A or B with Inhibitors

Body System; Reactions | # of adverse reactions; (n=1,939 treatments) | # of patients; (n=298 patients)
Body as a whole
Fever | 16 | 13
Platelets, Bleeding, and Clotting
Fibrinogen plasma decreased | 10 | 5
Cardiovascular
Hypertension | 9 | 6

Serious adverse reactions included thrombosis, pain, thrombophlebitis deep, pulmonary embolism, decreased therapeutic response, cerebrovascular disorder, angina pectoris, DIC, anaphylactic shock and abnormal hepatic function. The serious adverse reactions of DIC and therapeutic response decreased had a fatal outcome.

In two clinical trials evaluating safety and efficacy of NOVOSEVEN administration in the peri-operative setting in hemophilia A or B patients with inhibitors (N=51), the following serious adverse reactions were reported: acute post-operative hemarthrosis (n=1), internal jugular thrombosis adverse reaction (n=1), decreased therapeutic response (n=4).

Immunogenicity

There have been no confirmed reports of inhibitory antibodies against NOVOSEVEN or FVII in patients with congenital hemophilia A or B with alloantibodies.

The incidence of antibody formation is dependent on the sensitivity and specificity of the assay. Additionally, the observed incidence of antibody (including neutralizing antibody) positivity in an assay may be influenced by several factors including assay methodology, sample handling, timing of sample collection, concomitant medications, and underlying disease. For these reasons, comparison of the incidence of antibodies to NOVOSEVEN RT with the incidence of antibodies to other products may be misleading.

Congenital Factor VII Deficiency

Data collected from the compassionate/emergency use programs, the published literature, a pharmacokinetics study, and the Hemophilia and Thrombosis Research Society^2 (HTRS) registry showed that 75 patients with Factor VII deficiency had received NOVOSEVEN: 70 patients for 124 bleeding episodes, surgeries, or prophylaxis; 5 patients in the pharmacokinetics trial. The following adverse reactions were reported: intracranial hypertension (n=1), IgG antibody against rFVIIa and FVII (n=1), localized phlebitis (n=1).

Immunogenicity

In 75 patients with factor FVII deficiency treated with NOVOSEVEN RT, one patient developed IgG antibody against rFVIIa and FVII. Patients with factor VII deficiency treated with NOVOSEVEN RT should be monitored for factor VII antibodies.

The incidence of antibody formation is dependent on the sensitivity and specificity of the assay. Additionally, the observed incidence of antibody (including neutralizing antibody) positivity in an assay may be influenced by several factors including assay methodology, sample handling, timing of sample collection, concomitant medications, and underlying disease. For these reasons, comparison of the incidence of antibodies to NOVOSEVEN RT with the incidence of antibodies to other products may be misleading.

Acquired Hemophilia

Data collected from four compassionate use programs, the HTRS registry, and the published literature showed that 139 patients with acquired hemophilia received NOVOSEVEN for 204 bleeding episodes, surgeries and traumatic injuries. Of these 139 patients, 6 patients experienced 8 serious adverse reactions. Serious adverse reactions included shock (n=1), cerebrovascular accident (n=1) and thromboembolic events (n=6) which included cerebral artery occlusion, cerebral ischemia, angina pectoris, myocardial infarction, pulmonary embolism and deep vein thrombosis. Three of the serious adverse reactions had a fatal outcome.

Glanzmann’s Thrombasthenia

Data collected from the Glanzmann’s Thrombasthenia Registry (GTR) and the HTRS registry showed that 140 patients with Glanzmann’s thrombasthenia received NOVOSEVEN RT for 518 bleeding episodes, surgeries or traumatic injuries. The following adverse reactions were reported: deep vein thrombosis (n=1), headache (n=2), fever (n=2), nausea (n=1), and dyspnea (n=1).

6.2 Postmarketing Experience

Adverse reactions reported during postmarketing period were similar in nature to those observed during clinical trials and include reports of thromboembolic adverse events.

7 DRUG INTERACTIONS

- Avoid simultaneous use of activated prothrombin complex concentrates.
- Do not mix NOVOSEVEN RT with infusion solutions.
- Thrombosis may occur if NOVOSEVEN RT is administered concomitantly with Coagulation Factor XIII. [See Warnings and Precautions (5.1) and Nonclinical Toxicology (13.2)]

8 USE IN SPECIFIC POPULATIONS

8.1 Pregnancy

Risk Summary

There are no adequate and well-controlled studies using NOVOSEVEN RT in pregnant women to determine whether there is a drug-associated risk.

Treatment of rats and rabbits with NOVOSEVEN in reproduction studies has been associated with mortality at doses up to 6 mg per kg body weight and 5 mg per kg body weight respectively. At 6 mg per kg body weight in rats, the abortion rate was 0 out of 25 litters; in rabbits at 5 mg per kg body weight, the abortion rate was 2 out of 25 litters. Twenty-three out of 25 female rats given 6 mg per kg body weight of NOVOSEVEN gave birth successfully, however, two of the 23 litters died during the early period of lactation. No evidence of teratogenicity was observed after dosing with NOVOSEVEN.

In the U.S. general population, the estimated background risk of major birth defect and miscarriage in clinically recognized pregnancies is 2-4% and 15-20%, respectively.

8.2 Lactation

Risk Summary

There is no information regarding the presence of NOVOSEVEN RT in human milk, the effect on the breastfed infant, and the effects on milk production. The developmental and health benefits of breastfeeding should be considered along with the mother’s clinical need for NOVOSEVEN RT and any potential adverse effects on the breastfed infant from NOVOSEVEN RT or from the underlying maternal condition.

8.4 Pediatric Use

Clinical trials enrolling pediatric patients were conducted with dosing determined according to body weight and not according to age.

Hemophilia A or B with Inhibitors

During the investigational phase of product development NOVOSEVEN was used in 16 children aged 0 to <2 years for 151 bleeding episodes, 27 children aged 2 to <6 years for 140 bleeding episodes, 43 children aged 6 to <12 for 375 bleeding episodes and 30 children aged 12 to 16 years for 446 bleeding episodes.

In a double-blind, randomized comparison trial of two dose levels of NOVOSEVEN in the treatment of joint, muscle and mucocutaneous hemorrhages in hemophilia A and B patients with and without inhibitors 20 children aged 0 to <12 and 8 children aged 12 to 16 were treated with NOVOSEVEN in doses of 35 or 70 micrograms per kg dose. Treatment was assessed as effective (definite relief of pain/tenderness as reported by the patient and/or a measurable decrease of the size of the hemorrhage and/or arrest of bleeding within 8 hours [rated as excellent = 51%], within 8-14 hours [rated as effective = 18%] or after 14 hours [rated as partially effective = 25%]) in 94% of the patients.

NOVOSEVEN was used in two trials in surgery. In a dose comparison 22 children aged 0 to 16 years were treated with NOVOSEVEN. Effective intraoperative hemostasis (defined as bleeding that had stopped completely or had decreased substantially [rated as effective = 86%] or bleeding that was reduced but continued [rated as partially effective = 9%]) was achieved in 21/22 (95%) patients. Effective hemostasis was achieved in 10/10 (100%) patients in the 90 mcg/kg dose group and 10/12 (83%) in the 35 mcg/kg dose group at 48 hours; effective hemostasis was achieved in 10/10 (100%) in the 90 mcg/kg dose group and 9/12 (75%) in the 35 mcg/kg dose group at 5 days.

In the surgery trial comparing bolus (BI) and continuous infusion (CI) 6 children aged 10 to 15 years participated, 3 in each group. Both regimens were 100% effective (defined as bleeding has stopped completely, or decreased substantially) intra-operatively, through the first 24 hours and at day 5. At the end of the study period (Postoperative day 10 or discontinuation of therapy) hemostasis in two patients in the BI group was rated effective and hemostasis in one patient was rated as ineffective (defined as bleeding is the same or has worsened). Hemostasis in all three patients in the CI group was rated as effective.

Adverse drug reactions in pediatric patients were similar to those previously reported in clinical trials with NOVOSEVEN, including one thrombotic event in a 4 year old with internal jugular vein thrombosis after port-a-cath placement which resolved.

Congenital Factor VII deficiency

In published literature, compassionate use trials and registries on use of NOVOSEVEN in congenital Factor VII deficiency, NOVOSEVEN was used in 24 children aged 0 to <12 years and 7 children aged 12 to 16 years for 38 bleeding episodes, 16 surgeries and 8 prophylaxis regimens. Treatment was effective in 95% of bleeding episodes (5% not rated) and 100% of surgeries. No thrombotic events were reported. A seven-month old exposed to NOVOSEVEN and various plasma products developed antibodies against FVII and rFVIIa [see Adverse Reactions (6.1) and Overdosage (10)].

Glanzmann’s Thrombasthenia

In the Glanzmann’s Thrombasthenia Registry, NOVOSEVEN was used in 43 children aged 0 to 12 years for 157 bleeding episodes and in 15 children aged 0 to 12 years for 19 surgical procedures. NOVOSEVEN was also used in 8 children aged >12 to 16 years for 17 bleeding episodes and in 3 children aged >12 to 16 years for 3 surgical procedures. Efficacy of regimens including NOVOSEVEN was evaluated by independent adjudicators as 93.6% and 100% for bleeding episodes in children aged 0 to 12 years and >12 to 16 years, respectively. Efficacy in surgical procedures was evaluated as 100% for all surgical procedures in children aged 0 to 16 years. No adverse reactions were reported in Glanzmann’s thrombasthenia children.

[See Clinical Studies (14)]

8.5 Geriatric Use

Clinical studies of NOVOSEVEN RT in congenital factor deficiencies and Glanzmann’s thrombasthenia did not include sufficient numbers of subjects aged 65 and over to determine whether they respond differently from younger subjects.

10 OVERDOSAGE

Dose limiting toxicities of NOVOSEVEN RT have not been investigated in clinical trials. The following are examples of accidental overdose.

- One newborn female with congenital factor VII deficiency was administered an overdose of NOVOSEVEN (single dose: 800 micrograms per kg body weight). Following additional administration of NOVOSEVEN and various plasma products, antibodies against rFVIIa were detected, but no thrombotic complications were reported.
- One Factor VII deficient male (83 years of age, 111.1 kg) received two doses of 324 micrograms per kg body weight (10-20 times the recommended dose) and experienced a thrombotic event (occipital stroke).
- One hemophilia B patient (16 years of age, 68 kg) received a single dose of 352 micrograms per kg body weight and one hemophilia A patient (2 years of age, 14.6 kg) received doses ranging from 246 micrograms per kg body weight to 986 micrograms per kg body weight on five consecutive days. There were no reported complications in either case.

11 DESCRIPTION

NOVOSEVEN RT, Coagulation Factor VIIa (Recombinant) is a sterile, white lyophilized powder of recombinant human coagulation factor VIIa (rFVIIa) for reconstitution for intravenous injection. The product is supplied as single‑dose vials containing the following:

Contents | 1 mg Vial | 2 mg Vial | 5 mg Vial | 8 mg Vial
rFVIIa | 1000 micrograms | 2000 micrograms | 5000 micrograms | 8000 micrograms
sodium chloride* | 2.34 mg | 4.68 mg | 11.7 mg | 18.72 mg
calcium chloride dihydrate* | 1.47 mg | 2.94 mg | 7.35 mg | 11.76 mg
Glycylglycine | 1.32 mg | 2.64 mg | 6.60 mg | 10.56 mg
polysorbate 80 | 0.07 mg | 0.14 mg | 0.35 mg | 0.56 mg
Mannitol | 25 mg | 50 mg | 125 mg | 200 mg
Sucrose | 10 mg | 20 mg | 50 mg | 80 mg
Methionine | 0.5 mg | 1.0 mg | 2.5 mg | 4 mg
*per mg of rFVIIa: 0.4 mEq sodium, 0.01 mEq calcium

NOVOSEVEN RT also contains trace amounts of proteins derived from the manufacturing and purification processes such as mouse IgG (maximum of 1.2 ng/mg), bovine IgG (maximum of 30 ng/mg), and protein from BHK-cells and media (maximum of 19 ng/mg).

The diluent for reconstitution of NOVOSEVEN RT is a 10 mmol solution of histidine in water for injection and is supplied as a clear colorless solution in a vial or pre-filled diluent syringe. After reconstitution with the appropriate volume of histidine diluent, each vial contains approximately 1 mg/mL NOVOSEVEN RT (corresponding to 1000 micrograms/mL). The reconstituted solution is a clear colorless solution with a pH of approximately 6.0 and contains no preservatives.

Recombinant coagulation Factor VIIa (rFVIIa), the active ingredient in NOVOSEVEN RT, is a vitamin K‑dependent glycoprotein consisting of 406 amino acid residues with an approximate molecular mass of 50 kDa). It is structurally similar to endogenous human coagulation factor VIIa.

The gene for human coagulation factor VII (FVII) is cloned and expressed in baby hamster kidney cells (BHK cells). Recombinant FVII is secreted into the culture media (containing newborn calf serum) in its single-chain form and then proteolytically converted by autocatalysis to the active two-chain form, rFVIIa, during a chromatographic purification process. The purification process has been demonstrated to remove exogenous viruses (MuLV, SV40, Pox virus, Reovirus, BEV, IBR virus). No human serum or other proteins are used in the production or formulation of NOVOSEVEN RT.

12 CLINICAL PHARMACOLOGY

12.1 Mechanism of Action

NOVOSEVEN RT is recombinant Factor VIIa and, when complexed with tissue factor can activate coagulation Factor X to Factor Xa, as well as coagulation Factor IX to Factor IXa. Factor Xa, in complex with other factors, then converts prothrombin to thrombin, which leads to the formation of a hemostatic plug by converting fibrinogen to fibrin and thereby inducing local hemostasis. This process may also occur on the surface of activated platelets.

12.2 Pharmacodynamics

The effect of NOVOSEVEN RT upon coagulation in patients with or without hemophilia has been assessed in different model systems. In an in vitro model of tissue-factor-initiated blood coagulation (Figure A),^3 the addition of rFVIIa increased both the rate and level of thrombin generation in normal and hemophilia A blood, with an effect shown at rFVIIa concentrations as low as 10 nM. In this model, fresh human blood was treated with corn trypsin inhibitor (CTI) to block the contact pathway of blood coagulation. Tissue factor (TF) was added to initiate clotting in the presence and absence of rFVIIa for both types of blood.

In a separate model, and in line with previous reports,^4 escalating doses of rFVIIa in hemophilia plasma demonstrate a dose-dependent increase in thrombin generation (Figure B). In this model, platelet rich normal and hemophilia plasma was adjusted with autologous plasma to 200,000 platelets/microliter. Coagulation was initiated by addition of tissue factor and CaCl2. Thrombin generation was measured in the presence of a thrombin substrate and various added concentrations of rFVIIa.

Figure A

Figure B

12.3 Pharmacokinetics

Healthy Subjects

The pharmacokinetics of NOVOSEVEN was investigated in 35 healthy subjects (17 Caucasian, 18 Japanese, 16 men, 19 women) in a dose-escalation study. Subjects were dosed with 40, 80 and 160 micrograms per kg NOVOSEVEN.^5 No effect of gender or ethnicity on the pharmacokinetics of NOVOSEVEN was observed. Range of mean PK parameters across dose groups are shown in Table 4.

The products NOVOSEVEN® and NOVOSEVEN® RT were found to be pharmacokinetically equivalent in a study of 22 patients receiving single doses of both formulations.^6 Mean PK parameters for NOVOSEVEN® RT are shown in Table 4.

Hemophilia A or B

Single dose pharmacokinetics of NOVOSEVEN (17.5, 35, and 70 micrograms per kg) was studied in 15 subjects with hemophilia A or B in non-bleeding and bleeding state.^7 Median PK parameters (non-bleeding state) are shown in Table 4.

In a bolus single-dose pharmacokinetic study, 6 male adults (90 micrograms per kg) and 12 male pediatric (2-12 years) patients (crossover, 90 and 180 micrograms per kg) with severe hemophilia A (10 of 18 subjects had inhibitors to factor VIII) received NOVOSEVEN.^8 Compared with the adults, body weight normalized clearance of NOVOSEVEN in children 2-5 years and 6-12 years was higher by 82% and 42%, respectively. Pharmacokinetic parameters for children with Hemophilia are shown in Table 5.

Congenital Factor VII deficiency

Single dose pharmacokinetics of NOVOSEVEN in 5 patients with severe congenital Factor VII deficiency (<1%), at doses of 15 and 30 micrograms per kg body weight, showed no significant difference between the two doses. Mean PK parameters for the two doses are shown in Table 4.

Table 4: Single Dose Pharmacokinetic Parameters in Healthy Subjects, Patients With Hemophilia A and B, and Patients With FVII Deficiency (Mean (SD))

 | Healthy Subjects |  | Hemophilia A or B |  | FVII Deficiency^9
Formulation (n) | rFVIIa (n=35)5a | rFVIIa-25C (n=22)6b,c | rFVIIa (n=15)^7 | rFVIIa (n=6)8e | rFVIIa (n=5)9c
Ages | 20-45 | 22-44 | 15-63 | 30-45 | 20-43
Doses (mcg/kg) | 40, 80, 160 | 90 | 17.5, 35, 70 | 90 | 30
AUC (h*U/mL) | 71.46, 76.91* | 113.26 (17.36)d | 53.31 (20.27)** | 2.45 (0.73) | 23.70 (7.23)d
CL (mL/h) | 1953-2516 | 3077 (438) | NA | 2767 (385) | NA
CL (mL/h/kg) | 33-37 | 40.43 (6.23) | 33.84 (11.72) | 37.6 (13.1) | 67.7 (17.9)
t½ (h) | 3.9-6.0 | 3.54 (0.28) | 2.72 (0.54) | 3.2 (0.3) | 2.62 (0.63)
Vss (mL/kg) | 130-165 | 122.96 (20.42) | 108.86 (37.15) | 121 (30) | 230 (70)
MRT (h) | 3.66-4.98 | 3.05 (0.27) | 3.33 (0.64) | 3.31 (0.38) | 3.46 (0.64)
IR ([U/dL]/[U/kg]) | 0.89-1.04 | 1.18 (0.16)c | NA | 0.94 (0.16) | 0.53 (0.2)c

*Based on the 80 mcg/kg dose
  ** Based on the 70 mcg/kg dose
  NA: Not available
  AUC: Area under the curve from time 0 to infinity; CL: Clearance; t ½: terminal half-life; Vss: Volume of distribution at steady-state; MRT: mean residence time; IR: Incremental recovery; rFVIIa: NOVOSEVEN® original formulation; rFVIIa-25C: NOVOSEVEN® RT
  a: Results are for both males and females. The column presents ranges over ethnicity and gender.
  b: Study demonstrated bioequivalence of rFVIIa and rFVIIa-25C (NOVOSEVEN® RT)
c: FVIIa assay used: units in IU
d: AUC in h*IU/mL
e: Includes patients with and without inhibitors

Table 5: Single Dose Pharmacokinetic Parameters in Hemophilia A Patients With and Without Inhibitors (Mean (SD))

 | Hemophilia A
Formulation/ inhibitor status/ age group (n) | rFVIIa, without inhibitors, age ≤5 years; (n=3)^8 | rFVIIa, with; inhibitors; age ≤5 years; (n=2)^8 | rFVIIa, without inhibitors; age 6-12 years; (n=3)^8 | rFVIIa, with inhibitors; age 6-12 years; (n=4)^8 | rFVIIa, without inhibitors; Adults; (n=2)^8 | rFVIIa, with inhibitors; Adults; (n=4)^8
Ages (years) | 2-5 | 4 | 7-10 | 7-12 | 30-32 | 32-45
Weight (kg) | 14-17 | 22-26 | 25-38 | 25-68 | 72-97 | 54-89
Doses (mcg/kg) | 90, 180 | 90, 180 | 90, 180 | 90, 180 | 90 | 90
AUC (h*U/ mL) | 1.26 (0.09)* | 1.51 (0.25)* | 1.68 (0.24)* | 1.64 (0.31)* | 2.92 (0.80) | 2.13 (0.62)
CL (mL/h) | 1131 (114) | 1387 (75) | 1878 (499) | 1668 (510) | 2477 (162) | 2960 (378)
CL (mL/h/kg) | 73 (8) | 61 (9) | 55 (7) | 52 (12) | 30 (8) | 43 (15)
t½ (h) | 2.6 (0.9) | 1.9 (0.6) | 3.0 (1.1) | 3.0 (0.5) | 3.3 (0.3) | 3.2 (0.3)
Vss (mL/kg) | 191 (44) | 145 (1) | 173 (39) | 149 (22) | 108 (18) | 130 (37)
MRT (h) | 2.6 (0.5) | 2.4 (0.4) | 3.1 (0.5) | 2.9 (0.3) | 3.62 (0.40) | 3.09 (0.20)
IR ([IU/dL]/[U/kg]) | 0.59 (0.06) | 0.75 (0.12) | 0.75 (0.35) | 0.76 (0.20) | 1.01 (0.08) | 0.89 (0.20)

*Based upon the 90 mcg/kg dose
AUC: Area under the curve from time 0 to infinity; CL: Clearance; t ½: terminal half-life; Vss: Volume of distribution at steady state; MRT: mean residence time; IR: Incremental recovery; rFVIIa: (NOVOSEVEN® original formulation)

13 NONCLINICAL TOXICOLOGY

13.1 Carcinogenesis, Mutagenesis, Impairment of Fertility

Two mutagenicity studies have given no indication of carcinogenic potential for NOVOSEVEN. The clastogenic activity of NOVOSEVEN was evaluated in both in vitro studies (i.e., cultured human lymphocytes) and in vivo studies (i.e., mouse micronucleus test). Neither of these studies indicated clastogenic activity of NOVOSEVEN. Other gene mutation studies have not been performed with NOVOSEVEN RT (e.g., Ames test). No chronic carcinogenicity studies have been performed with NOVOSEVEN RT.

A reproductive study in male and female rats at dose levels up to 3.0 mg per kg per day had no effect on mating performance, fertility, or litter characteristics.

Treatment of rats and rabbits with NOVOSEVEN in reproduction studies has been associated with mortality at doses up to 6 mg per kg and 5 mg per kg. At 6 mg per kg in rats, the abortion rate was 0 out of 25 litters; in rabbits at 5 mg per kg, the abortion rate was 2 out of 25 litters. Twenty-three out of 25 female rats given 6 mg per kg of NOVOSEVEN gave birth successfully, however, two of the 23 litters died during the early period of lactation. No evidence of teratogenicity was observed after dosing with NOVOSEVEN.

13.2 Animal Toxicology and/or Pharmacology

In a monkey cardiovascular safety pharmacology model evaluating the combination of excessive doses of Coagulation Factor XIII A-Subunit (Recombinant) (585 IU/kg, 17 times the expected human dose) in combination with rFVIIa (1000 mcg/kg, 11 times the expected human dose), one of the twelve monkeys died 4 hours after treatment due to thrombosis. Procoagulant risk factors, including 6 indwelling catheters per monkey and the induction of anesthesia, may have complicated the study results. It is unclear whether the mortality was related to the overdose of one or both products, or a specific interaction between them. Nonclinical and clinical studies with the combination of rFXIII and NOVOSEVEN RT at recommended human doses have not been performed.

14 CLINICAL STUDIES

14.1 Hemophilia A or B with Inhibitors

The largest number of patients (N=483) who received NOVOSEVEN during the investigational phase of product development were in an open protocol study ^10,11,12 that began enrollment in 1988, shortly after the completion of the pharmacokinetic study. These patients included persons with hemophilia types A or B (with or without inhibitors), persons with acquired inhibitors to Factor VIII or Factor IX, and a few FVII deficient patients. The clinical situations were diverse and included muscle/joint bleeds, mucocutaneous bleeds, surgical prophylaxis, intracerebral bleeds, and other emergent situations.

A double-blind, randomized comparison trial^13 of two dose levels of NOVOSEVEN in the treatment of joint, muscle and mucocutaneous hemorrhages in hemophilia A and B patients with and without inhibitors was conducted in 78 patients who received NOVOSEVEN in treatment centers within 4 to 18 hours after experiencing a bleed. Thirty-five patients were treated at the 35 micrograms per kg dose (59 joint, 15 muscle and 5 mucocutaneous bleeding episodes) and 43 patients were treated at the 70 micrograms per kg dose (85 joint and 14 muscle bleeding episodes). Dosing was repeated at 2.5 hour intervals but ranged up to four hours for some patients. Efficacy was assessed at 12 ± 2 hours or at end of treatment, whichever occurred first. Based on a subjective evaluation by the investigator, the respective efficacy rates for the 35 and 70 micrograms per kg groups were: excellent (definite relief of pain/tenderness as reported by the patient and/or a measurable decrease of the size of the hemorrhage and/or arrest of bleeding within 8 hours) 59% and 60%, effective (definite relief of pain/tenderness as reported by the patient and/or a measurable decrease of the size of the hemorrhage and/or arrest of bleeding within 8-14 hours) 12% and 11%, and partially effective (definite relief of pain/tenderness as reported by the patient and/or a measurable decrease of the size of the hemorrhage and/or arrest of bleeding after 14 hours) 17% and 20%. The average number of injections required to achieve hemostasis was 2.8 and 3.2 for the 35 and 70 micrograms per kg groups, respectively.

Two clinical trials were conducted to evaluate the safety and efficacy of NOVOSEVEN administration during and after surgery in hemophilia A or B patients with inhibitors. One of the studies was a randomized, double-blind, parallel group clinical trial (28 patients with hemophilia A or B and inhibitors and one patient with acquired inhibitor to FVIII, undergoing major or minor surgical procedures).^14 Patients received bolus intravenous NOVOSEVEN (either 35 micrograms per kg, N=15; or 90 micrograms per kg, N=14) prior to surgery, intra-operatively as required, then every 2 hours for the following 48 hours beginning at closure of the wound. Additional doses were administered every 2 to 6 hours up to an additional 3 days to maintain hemostasis. After a maximum of 5 days of double-blind treatment, therapy could be continued in an open-label manner if necessary (90 micrograms per kg NOVOSEVEN every 2-6 hours) (Table 6). Efficacy was assessed during the intra-operative period, and post-operatively from the time of wound closure (Hour 0) through Day 5.

Table 6: Dosing by Surgery Category

 |  | Major Surgery |  |  |  | Minor Surgery
 |  | 35 μg/kg [µg/kg = micrograms per kg body weight]; (n = 5) |  | 90 μg/kg; (n = 6) |  | 35 μg/kg; (n = 10) |  | 90 μg/kg; (n = 8)
Days of dosing, median (range) |  | 15 (2-26) |  | 9.5 (8-17) |  | 4 (3-6) |  | 6 (3-13)
No. injections, median (range) |  | 135 (11-186) |  | 81 (71-128) |  | 29.5 (24-44) |  | 39.5 (26-98)
Median total dose, mg (range) |  | 656 (31-839) |  | 569 (107-698) |  | 45.5 (14-171) |  | 67 (31-122)

Intraoperative hemostasis was achieved in 28/29 (97%) patients. Satisfactory hemostasis was achieved in 14/14 (100%) patients in the 90 mcg/kg dose group and 11/15 (73%) in the 35 mcg/kg dose group at 48 hours; satisfactory hemostasis was achieved in 13/14 (93%) in the 90 mcg/kg dose group and 11/15 (73%) in the 35 mcg/kg dose group at 5 days. Twenty-three patients successfully completed the entire study including 13/14 (93%) achieving successful hemostasis through study completion (up to day 26) in the 90 mcg/kg dose group.

Another open-label, randomized, parallel trial was conducted to compare the safety and efficacy of bolus intravenous (BI) injection (N=12) and continuous intravenous (CI) infusion (N=12) administration of NOVOSEVEN in 23 hemophilia A or B patients with inhibitors and one patient with acquired hemophilia who were undergoing elective major surgery. Table 7 provides the overview of dosing by treatment group for BI and CI.

Table 7: Dosing by Treatment Group

 |  | Bolus Injection | Continuous Infusion
 |  | 90 micrograms/kg (n = 12)a | 50 micrograms/kg/h (n = 12)
Days of dosing, median (range) |  | 10 (4-15)b | 10 (2-116)
No. bolus injections, median (range) |  | 38 (36-42) | 1.5 (0-7)
No. of additional bolus injections, median (range) |  | 0 (0-3) | 0 (0-4)
Mean total dose, mg |  | 237.5 | 292.2

a Includes one patient with acquired hemophilia

b Includes dosing during the follow-up period after the 10-day study period.

Intraoperative hemostasis was reported as effective in all BI and CI treated patients. BI regimen was 100% effective through the first 24 hours, and was 92% effective at day 5. CI regimen was 83% effective through the first 24 hours, and was 83% effective at day 5. At the end of the study period (Post operative day 10 or discontinuation of therapy), hemostatic efficacy in the BI and CI arms was 9/12 (75%) and 10/12 (83%), respectively.

14.2 Congenital Factor VII Deficiency

Data were collected from the published literature, compassionate use trials and registries for 70 patients with Factor VII deficiency treated with NOVOSEVEN for 124 bleeding episodes, surgeries, or prophylaxis regimens. Thirty-two of these patients were enrolled in emergency and compassionate use trials conducted by Novo Nordisk (43 non-surgical bleeding episodes, 26 surgeries); 35 were reported in the published literature (20 surgeries, 10 non-surgical bleeding episodes, 4 cases of caesarean section or vaginal birth, and 10 cases of long-term prophylaxis, and 1 case of on-demand therapy); and 3 were from a registry maintained by the Hemophilia and Thrombosis Research Society (9 bleeding episodes, 1 surgery). Dosing ranged from 6 to 98 micrograms per kg administered every 2-12 hours (except for prophylaxis, where doses were administered from 2 times per day up to 2 times per week). Patients were treated with an average of 1-10 doses. Treatment was effective (bleeding stopped or treatment was rated as effective by the physician) in 93% of episodes (90% for trial patients, 98% for published patients, 90% for HTRS registry patients).

14.3 Acquired Hemophilia

Data were collected from four studies in a compassionate use program conducted by Novo Nordisk and the Hemophilia and Thrombosis Research Society (HTRS) registry. The studies were not designed to select doses or compare first-line efficacy or efficacy when used after failure of other hemostatic agents (salvage treatment). A total of 70 patients with acquired hemophilia were treated with NOVOSEVEN for 113 bleeding episodes, surgeries, or traumatic injuries. Sixty-one of these patients were from the compassionate use program with 100 bleeding episodes (68 non-surgical and 32 surgical bleeding episodes) and 9 patients were from the HTRS registry with 13 bleeding episodes (8 non-surgical, 3 surgical and 2 episodes classified as other). Concomitant use of other hemostatic agents occurred in 29/70 (41%); 13 (19%) received more than one hemostatic agent. The most common hemostatic agents used were antifibrinolytics, Factor VIII and activated prothrombin complex concentrates.

The mean dose of NOVOSEVEN administered was 90 micrograms per kg (range: 31 to 197 micrograms per kg); the mean number of injections per day was 6 (range: 1 to 10 injections per day). Overall efficacy (i.e., effective and partially effective outcomes) was 87/112 (78%); with 77/100 (77%) efficacy in the compassionate use programs and 10/12 (83%) efficacy in the HTRS registry. In the compassionate use programs, overall efficacy for the first-line treatment was 38/44 (86%) compared to 39/56 (70%) when used as salvage treatment (Table 8).

Table 8: Efficacy of NOVOSEVEN in Compassionate Use Programs and HTRS Registry

Outcomea | Total
Effective | 67
Partial | 20
Ineffective | 17
Unknown | 8
No. of Bleeding Episodes | 112b

a Outcome assessed at end of treatment, last observation carried forward.

b One patient in the HTRS registry was excluded from efficacy analysis since NOVOSEVEN was used to maintain hemostasis after bleeding had been controlled.

14.4 Glanzmann’s Thrombasthenia

Data were collected from the Glanzmann’s Thrombasthenia Registry (GTR), the Hemostasis and Thrombosis Research Society (HTRS) registry, and the published literature. The GTR was observational, and therefore not designed to select doses. The GTR captured data for 218 Glanzmann’s thrombasthenia patients with 1073 bleeding and surgical events. An independent adjudication committee assessed clinical refractoriness and antibody status based upon historical data from investigators, patterns of treatment, and treatment responses when only platelets were used. Adjudicators defined clinical refractoriness as lack of platelet response. Patients with apparent response to platelets only were not considered refractory, even if coded as such by investigators. Antibody status included GPIIb/IIIa, HLA, and unspecified platelet-specific antibodies. Efficacy was evaluated on a two-point scale (clinical assessment of success or failure of treatment regimen as a whole, blinded and unblinded to investigator coded outcome) in 190 patients with 755 episodes requiring systemic hemostatic therapy (151 patients with 564 severe bleeding episodes, 90 patients with 192 surgeries, one episode was classified as both). Of these a total of 92 patients were treated with NOVOSEVEN RT for 266 bleeding episodes and 77 patients treated for 160 surgical procedures. A large number of bleeding episodes were treated with NOVOSEVEN RT alone (109/266 (41%) events).

The median dose of NOVOSEVEN RT administered for bleeding episodes and surgical procedures was 90 micrograms per kg and the median interval between doses was 3 hours.

For all subjects, concomitant use of other hemostatic agents occurred in 157/266 (59%) bleeding episodes and 94/160 (59%) surgical procedures.

The majority of NOVOSEVEN RT treated bleeding episodes were in pediatric patients (65%; children and adolescents, 0-16 yrs.).

Of the 266 bleeding episodes treated with NOVOSEVEN RT, the most common types of bleeding episodes were: epistaxis (116, 43.6%), gum bleeding (48, 18.0%), menorrhagia (36, 13.5%), tooth/dental extraction related (29, 10.9%), and gastrointestinal (23, 8.6%).

Of the patients treated with NOVOSEVEN RT for surgical procedures, 86% were adults (> 16 years). Major surgery was defined as any invasive operative procedure in which, body cavity was entered, mesenchymal barrier was crossed, facial plane was opened, organ was removed or normal anatomy was operatively altered. Minor surgery was defined as any invasive operative procedure in which only skin, mucous membranes, or superficial connective tissue were manipulated. Surgical procedures treated with NOVOSEVEN RT included minor (134/160; 83.8%) and major (26/160, 16.3%) procedures. Dental procedures were most common (106, 66.3%), followed by endoscopy (12, 7.5%), nasal procedures (8, 5.0%), excision (7, 4.4%), GI surgery (7, 4.4%) and orthopedic procedures (6, 3.8%). Most surgeries were elective (147, 91.9%), with a few emergency (7, 4.4%) or unspecified (6).

Overall, treatment with NOVOSEVEN RT was successful in 94.4% of bleeding episodes (Table 9) and 99.4% of surgical procedures (Table 10). Adjudicator-rated efficacy was consistent across treatment regimens, bleed and surgery types, age, and refractory/antibody status. Treatment with NOVOSEVEN RT was successful in patients with clinical refractoriness with or without platelet-specific antibodies in 94.9% of bleeding episodes and 98.6% of surgical procedures. In patients without refractoriness or platelet-specific antibodies, treatment with NOVOSEVEN RT was comparable to treatment with platelets.

Table 9: Adjudicator Evaluation of Efficacy – Bleeding Episodes for GTR Data

 | No. of patientsc | No. of episodes | Success | Failure | Insufficient data | No Consensus
All NOVOSEVEN* | 92 | 266 | 251 (94.4) | 4 (1.5) | 6 (2.3) | 5 (1.9)
By Treatment Regimen
NOVOSEVEN only | 44 | 109 | 101 (92.7) | 2 (1.8) | 4 (3.7) | 2 (1.8)
NOVOSEVEN ± Platelets ± Other hemostatic agents | 69 | 157 | 150 (95.5) | 2 (1.3) | 2 (1.3) | 3 (1.9)
By Antibody/Refractory Group
Refractoriness ± Platelet-specific antibodiesa,d | 31 | 79 | 75 (94.9) | 2 (2.5) | 2 (2.5) | 0 (0.0)
Platelet-specific-antibodiesa,d | 8 | 10 | 10 (100.0) | 0 (0.0) | 0 (0.0) | NA
Neither or unknownb,d | 57 | 177 | 166 (93.8) | 2 (1.1) | 4 (2.3) | 5 (2.8)

*All treatment regimens that included treatment with NOVOSEVEN

a includes GPIIb/IIIa, HLA, and unspecified platelet-specific antibodies

b Assumes no platelet-specific antibodies or refractoriness reported or antibody and refractory status unknown

c Patient numbers are not additive. Patients may have episodes with different treatment regimens and have more than one antibody/refractory status

d Treatment was NOVOSEVEN only for 26/79 episodes with refractoriness with or without antibodies, 2/10 episodes with platelet specific antibodies only, and 81/177 episodes with neither or unknown. The remainder received NOVOSEVEN with platelets and/or antifibrinolytic agents.

Table 10: Adjudicator Evaluation of Efficacy – Surgical Procedures for GTR Data

Treatment group | No. of patientsc | No. of procedures | Success | Insufficient datad
All NOVOSEVEN* | 77 | 160 | 159 (99.4) | 1 (0.6)
By Treatment Regimen
NOVOSEVEN only | 35 | 66 | 65 (98.5) | 1 (1.5)
NOVOSEVEN ± Platelets ± Other hemostatic agents | 57 | 94 | 94 (100.0) | 0 (0.0)
By Antibody/Refractory Group
Refractoriness ± Platelet-specific antibodiesa,e | 33 | 70 | 69 (98.6) | 1 (1.4)
Platelet-specific antibodiesa,e | 11 | 24 | 24 (100.0) | 0 (0.0)
Neither or unknownb,e | 36 | 66 | 66 (100) | 0 (0.0)

*All treatment regimens that included treatment with NOVOSEVEN

a includes GPIIb/IIIa, HLA, and unspecified platelet-specific antibodies

b Assumes no platelet-specific antibodies or refractoriness reported or antibody and refractory status unknown

c Patient numbers are not additive. Patients may have episodes with different treatment regimens and have more than one antibody/refractory status

d No reports of failure or lack of consensus was reported

e Treatment was NOVOSEVEN only for 22/70 episodes with refractoriness with or without antibodies, 13/24 episodes with platelet specific antibodies only, and 31/66 episodes with neither or unknown. The remainder received NOVOSEVEN with platelets and/or antifibrinolytic agents.

In HTRS, there were 7 patients that were treated with NOVOSEVEN RT for 23 bleeding episodes. Concomitant hemostatic agents were administered for 11 episodes (antifibrinolytics in 10 episodes). Treatment was reported effective in 21 of 23 (91.3%) episodes. In the other 2 episodes, bleeding was reported as slowed or no improvement, however in neither episode was further treatment reported. There were no surgical procedures reported in the HTRS registry.

15 REFERENCES

1. Hedner, U.: Dosing and Monitoring NOVOSEVEN ® Treatment, Haemostasis 1996; 26 (suppl 1): 102-108.
2. Parameswaran, R., et al.: Dose effect and efficacy of rFVIIa in the treatment of haemophilia patients with inhibitors: analysis from the Hemophilia and Thrombosis Research Society Registry, Haemophilia 2005; 11: 100-106.
3.Butenas, S., et al.: Mechanism of factor VIIa-dependent coagulation in hemophilia blood, Blood 2002; 99: 923-930. Figure A Copyright American Society of Hematology, used with permission.
4. Allen, G.A., et al.: The effect of factor X level on thrombin generation and the procoagulant effect of activated factor VII in a cell-based model of coagulation, Blood Coagulation and Fibrinolysis 2000; 11 (suppl 1): 3-7.
5. Fridberg M.J., et al.: A study of the pharmacokinetics and safety of recombinant activated factor VII in healthy Caucasian and Japanese subjects, Blood Coagulation and Fibrinolysis 2005; 16 (4): 259-266.
6. Bysted B.V., et al.: A randomized double-blind trial demonstrating bioequivalence of the current recombinant activated factor VII formulation and a new robust 25ºC stable formulation, Haemophilia 2007; 13, 527-532.
7. Lindley, C.M., et al.: Pharmacokinetics and pharmacodynamics of recombinant Factor VIIa, Clinical Pharmacology & Therapeutics 1994; 55 (6): 638-648.
8.Villar, A., et al.: Pharmacokinetics of activated recombinant coagulation factor VIIa (NOVOSEVEN®) in children vs. adults with haemophilia A, Haemophilia 2004; 10 (4):352-359.
9. Berretinni M.: Pharmacokinetic evaluation of recombinant, activated factor VII in patients with inherited factor VII deficiency. Haematologica 2001; 86:640-645.
10. Lusher, J., et al.: Clinical experience with recombinant Factor VIIa, Blood Coagulation and Fibrinolysis 1998; 9: 119-128.
11. Bech, M.R.: Recombinant Factor VIIa in Joint and Muscle Bleeding Episodes, Haemostasis 1996; 26 (suppl 1): 135-138.
12. Lusher, J.M.: Recombinant Factor VIIa (NOVOSEVEN ®) in the Treatment of Internal Bleeding in Patients with Factor VIII and IX Inhibitors, Haemostasis 1996; 26 (suppl 1): 124-130.
13. Lusher, J.M., et al.: A randomized, double-blind comparison of two dosage levels of recombinant factor VIIa in the treatment of joint, muscle and mucocutaneous haemorrhages in persons with hemophilia A and B, with and without inhibitor, Haemophilia 1998; 4: 790-798.
14. Shapiro A.D., et al: Prospective, Randomised Trial of Two Doses of rFVIIa (NOVOSEVEN ®) in Haemophilia Patients with Inhibitors Undergoing Surgery, Thrombosis and Haemostasis 1998; 80: 773-778.

16 HOW SUPPLIED/STORAGE AND HANDLING

How Supplied

NOVOSEVEN RT, Coagulation Factor VIIa (Recombinant), is supplied as a room temperature stable, white, lyophilized powder in single‑dose vials, one single-dose vial per carton. The diluent for reconstitution of NOVOSEVEN RT is a 10 mmol solution of L-histidine in water for injection and is supplied as a clear colorless solution, and referred to as the histidine diluent. The histidine diluent is provided in either a vial or pre-filled diluent syringe.

The amount of rFVIIa in milligrams and in micrograms is stated on the label.

NOVOSEVEN RT package containing 1 single-dose vial of NOVOSEVEN RT powder and 1 vial of histidine diluent:

Presentation | Carton NDC Number | Components
1 mg per vial; (1000 micrograms/vial) | NDC 0169 7010 01 | - NOVOSEVEN RT in a single-dose vial [NDC 0169-7017-11] - Histidine diluent in vial, 1.1 mL [NDC 0169-7001-98]
2 mg per vial; (2000 micrograms/vial) | NDC 0169 7020 01 | - NOVOSEVEN RT in a single-dose vial [NDC 0169-7027-11] - Histidine diluent in vial, 2.1 mL [NDC 0169-7002-98]
5 mg per vial; (5000 micrograms/vial) | NDC 0169 7050 01 | - NOVOSEVEN RT in a single-dose vial [NDC 0169-7057-11] - Histidine diluent in vial, 5.2 mL [NDC 0169-7005-98]
8 mg per vial; (8000 micrograms/vial) | NDC 0169 7040 01 | - NOVOSEVEN RT in a single-dose vial [NDC 0169-7047-11] - Histidine diluent in vial, 8.1 mL [NDC 0169-7004-98]

NOVOSEVEN RT with MixPro® package containing 1 single-dose vial of NOVOSEVEN RT powder and 1 pre-filled histidine diluent syringe with sterile vial adapter which serves as an alternative needleless reconstitution system:

Presentation | Carton NDC Number | Components
1 mg per vial; (1000 micrograms/vial) | NDC 0169 7201 01 | - NOVOSEVEN RT in a single-dose vial [NDC 0169-7211-11] - Pre-filled histidine diluent in syringe, 1 mL [NDC 0169-7011-98] - Vial adapter
2 mg per vial; (2000 micrograms/vial) | NDC 0169 7202 01 | - NOVOSEVEN RT in a single-dose vial [NDC 0169-7212-11] - Pre-filled histidine diluent in syringe, 2 mL [NDC 0169-7012-98] - Vial adapter
5 mg per vial; (5000 micrograms/vial) | NDC 0169 7205 01 | - NOVOSEVEN RT in a single-dose vial [NDC 0169-7215-11] - Pre-filled histidine diluent in syringe, 5 mL [NDC 0169-7015-98] - Vial adapter
8 mg per vial; (8000 micrograms/vial) | NDC 0169 7208 01 | - NOVOSEVEN RT in a single-dose vial [NDC 0169-7218-11] - Pre-filled histidine diluent in syringe, 8 mL [NDC 0169-7018-98] - Vial adapter

The NOVOSEVEN RT and histidine diluent vials are made of glass closed with a chlorobutyl rubber stopper not made with natural rubber latex, and covered with an aluminum cap. The pre-filled diluent syringes are made of glass, with a siliconised bromobutyl rubber plunger not made with natural rubber latex. The closed vials and pre-filled diluent syringes are equipped with a tamper-evident snap-off cap which is made of polypropylene. A vial adapter with 25 micrometer filter is provided with the pre-filled diluent syringe.

Storage and Handling

Prior to reconstitution, store NOVOSEVEN RT powder and histidine diluent between 2-25°C (36-77°F). Do not freeze. Store protected from light. Do not use past the expiration date.

After reconstitution, store NOVOSEVEN RT either at room temperature or refrigerated for up to 3 hours. Do not freeze reconstituted NOVOSEVEN RT or store in syringes.

17 PATIENT COUNSELING INFORMATION

Advise the patient:

- To read the FDA-approved patient labeling (Instructions for Use).
- About the early signs of hypersensitivity reactions, including hives, urticaria, tightness of the chest, wheezing, hypotension, and anaphylaxis.
- About the signs of thrombosis, including new onset swelling and pain in the limbs or abdomen, new onset chest pain, shortness of breath, loss of sensation or motor power, or altered consciousness or speech.
- To immediately seek medical help if any of the above signs or symptoms occur.
- To follow the recommendations in the FDA-approved patient labeling, regarding proper sharps disposal.

Version: 2020July-V20

PATENT Information: http://novonordisk-us.com/products/product-patents.html

Novo Nordisk® is a registered trademark of Novo Nordisk A/S.

NOVOSEVEN® is a registered trademark of Novo Nordisk Health Care AG.

MixPro® is a registered trademark of Novo Nordisk A/S.

Clave® and MicroClave® are registered trademarks of ICU Medical Inc.

InVision-Plus®, InVision-Plus CS®, InVision-Plus® Junior® are registered trademarks of RyMed Technologies, Inc.

Bionector® is a registered trademark of Vygon.

© 2020 Novo Nordisk

For information contact:

Novo Nordisk Inc.

800 Scudders Mill Road

Plainsboro, NJ 08536, USA

1-877-NOVO-777

www.NOVOSEVENRT.com

Manufactured by:

Novo Nordisk A/S

2880 Bagsvaerd, Denmark

License Number: 1261

Patient Package Insert

FDA Approved Patient Labeling

Instructions for Use

NovoSeven RT

Coagulation Factor VIIa (Recombinant)

Instructions on how to use NovoSeven® RT

READ THESE INSTRUCTIONS CAREFULLY BEFORE USING NOVOSEVEN® RT.

NovoSeven® RT is supplied as a powder. Before injection (administration) it must be mixed (reconstituted) with the liquid diluent supplied in the syringe. The liquid diluent is a histidine solution. The mixed NovoSeven® RT must be injected into your vein (intravenous injection). The equipment in this package is designed to mix and inject NovoSeven® RT.

You will also need an infusion set (tubing and butterfly needle), sterile alcohol swabs, gauze pads, and bandages.

Don’t use the equipment without proper training from your doctor or nurse.

Always use a clean and germ free (aseptic) technique. It is important that you wash your hands and ensure that the area around you is clean.

Don’t open the equipment until you are ready to use it.

The equipment is for single use only.

Single-dose vial. Discard unused portion.

Content

The package contains:

• Vial with NovoSeven® RT powder

• Vial adapter

• Pre-filled syringe with diluent

• Plunger rod (placed under the syringe)

Overview

1. Prepare the vial and the syringe

- Take out the number of NovoSeven® RT packages you need. Check the expiry date.
- Check the name and the color of the package, to make sure it contains the correct product.
- Wash your hands and dry them properly using a clean towel or air dry.
- Take the vial, the vial adapter and the pre-filled syringe out of the carton. Leave the plunger rod untouched in the carton.
- Bring the vial and the pre-filled syringe to room temperature (not above 98.6°F (37°C)). You can do this by holding them in your hands until they feel as warm as your hands.

- Remove the plastic cap from the vial. If the plastic cap is loose or missing, don’t use the vial.
- Wipe the rubber stopper on the vial with a sterile alcohol swab and allow it to dry for a few seconds before use. Don’t touch the rubber stopper after wiping it.

Don’t use the equipment if it has been dropped, or if it is damaged. Use a new package instead.

Don’t use the equipment if it is expired. Use a new package instead. The expiration date is printed on the outer carton and on the vial, the vial adapter and the pre-filled syringe.

Don’t dispose of any of the items until after you have injected the mixed solution.

2. Attach the vial adapter

- Remove the protective paper from the vial adapter.
Don’t take the vial adapter out of the protective cap.
If the protective paper is not fully sealed or if it is broken, don’t use the vial adapter.

- Place the vial on a flat and solid surface.
- Turn over the protective cap, and snap the vial adapter onto the vial.
Don’t touch the spike on the vial adapter.
Once attached, don’t remove the vial adapter from the vial.

- Lightly squeeze the protective cap with your thumb and index finger as shown.
Remove the protective cap from the vial adapter.
Don’t lift the vial adapter from the vial when removing the protective cap.

3. Attach the plunger rod and the syringe

- Grasp the plunger rod by the wide top end and take it out of the carton. Be careful not to touch the sides or the thread of the plunger rod. Keep holding the plunger rod at the wide top end.
- Immediately connect the plunger rod to the syringe by turning it clockwise into the rubber plunger inside the pre-filled syringe until resistance is felt.

- Remove the syringe cap from the pre-filled syringe by bending it down until the perforation breaks.
Don’t touch the syringe tip under the syringe cap.
If the syringe cap is loose or missing, don’t use the pre-filled syringe.

- Screw the pre-filled syringe securely onto the vial adapter until resistance is felt.

Avoid touching the sides of the plunger rod at any time.

4. Mix the powder with the diluent

- Hold the pre-filled syringe slightly tilted with the vial pointing downwards.
- Push the plunger rod to inject all the diluent into the vial.

- Keep the plunger rod pressed down and swirl the vial gently until all the powder is dissolved.
Don’t shake the vial as this will cause foaming.
- Check the mixed solution. It must be clear and colorless. If you notice visible particles or discoloration, don’t use it. Use a new package instead.

NovoSeven® RT is recommended to be used immediately after it is mixed.

If you cannot use the mixed NovoSeven® RT solution immediately, it can be kept in the vial, still with the vial adapter and the syringe attached, at room temperature or refrigerated for no longer than 3 hours.

Do not freeze mixed NovoSeven® RT solution or store it in syringes.

Keep mixed NovoSeven® RT solution out of direct light.

If your dose requires more than one vial, repeat step A to J with additional vials, vial adapters and pre-filled syringes until you have reached your required dose.

- Keep the plunger rod pushed completely in.
- Turn the syringe with the vial upside down.
- Stop pushing the plunger rod and let it move back on its own while the mixed solution fills the syringe.
- Pull the plunger rod slightly downwards to draw the mixed solution into the syringe. In case you only need part of the entire dose, use the scale on the syringe to see how much mixed solution you withdraw, as instructed by your doctor or nurse.
- While holding the vial upside down, tap the syringe gently to let any air bubbles rise to the top.
- Push the plunger rod slowly until all air bubbles are gone.

- Unscrew the vial adapter with the vial.

Caution: The pre-filled diluent syringe is made of glass with an internal tip diameter of 0.037 inches, and is compatible with a standard Luer-lock connector.

Some needleless connectors for intravenous catheters are incompatible with the glass diluent syringes (for example, certain connectors with an internal spike, such as Clave® /MicroClave®, InVision-Plus®, InVision-Plus CS®, InVision-Plus® Junior®, Bionector®), and their use can damage the connector and affect administration. To administer product through incompatible needleless connectors, withdraw reconstituted product into a standard 10 mL sterile Luer-lock plastic syringe.

If you have encountered any problems with attaching the pre-filled histidine diluent syringe to any Luer-lock compatible device, please contact Novo Nordisk at (877) 668-6777.

5. Inject the mixed solution

NovoSeven® RT is now ready to inject into your vein.

- Do not mix NovoSeven® RT with any other intravenous infusions or medications.
- Inject the mixed solution slowly over 2 to 5 minutes as instructed by your doctor or nurse.

Injecting the solution via a central venous access device (CVAD) such as a central venous catheter or subcutaneous port:

- Use a clean and germ free (aseptic) technique. Follow the instructions for proper use for your connector and central venous access device in consultation with your doctor or nurse.
- Injecting into a CVAD may require using a sterile 10 mL plastic syringe for withdrawal of the mixed solution and injection.
- If necessary, use 0.9% Sodium Chloride Injection, USP to flush the CVAD line before or after NovoSeven® RT injection.

The peel-off label found on the NovoSeven® RT vial can be used to record the lot number.

Disposal

- After injection, safely dispose of the syringe with the infusion set, the vial with the vial adapter, any unused NovoSeven® RT and other waste materials as instructed by your doctor or nurse.
Don’t throw it out with the ordinary household trash.

Don’t disassemble the vial and vial adapter before disposal.

Don’t reuse the equipment.

For full Prescribing Information please read the other insert included in this package.

Revised: 07/2020

PATENT information: http://novonordisk-us.com/products/product-patents.html

Novo Nordisk® is a registered trademark of Novo Nordisk A/S.

NovoSeven® is a registered trademark of Novo Nordisk Health Care AG.

Clave® and MicroClave® are registered trademarks of ICU Medical Inc.

InVision-Plus®, InVision-Plus CS®, InVision-Plus® Junior® are registered trademarks of RyMed Technologies, Inc.

Bionector® is a registered trademark of Vygon.

© 2020 Novo Nordisk

Manufactured by:

Novo Nordisk A/S

2880 Bagsvaerd, Denmark

License Number: 1261

Version: 20200710-v8

PACKAGE LABEL

Principal Display Panel 1 mg

NDC 0169 7010 01

List: 701001

NovoSeven® RT

Coagulation Factor VIIa

(Recombinant)

Room Temperature Stable

1 mg

For IV administration only

For human use only

Single dose vial

Administer within 3 hours of reconstitution

Contains no preservative

Rx only

novo nordisk®

PACKAGE LABEL

Principal Display Panel 2mg

NDC 0169 7020 01

List: 702001

NovoSeven® RT

Coagulation Factor VIIa

(Recombinant)

Room Temperature Stable

2 mg

For IV administration only

For human use only

Single dose vial

Administer within 3 hours of reconstitution

Contains no preservative

Rx only

novo nordisk®

PACKAGE LABEL

Principal Display Panel 5 mg

NDC 0169 7050 01

List: 705001

NovoSeven® RT

Coagulation Factor VIIa

(Recombinant)

Room Temperature Stable

5 mg

For IV administration only

For human use only

Single dose vial

Administer within 3 hours of reconstitution

Contains no preservative

Rx only

novo nordisk®

PACKAGE LABEL

Principal Display Panel 8 mg

NDC 0169 7040 01

List: 704001

NovoSeven® RT

Coagulation Factor VIIa

(Recombinant)

Room Temperature Stable

8 mg

For IV administration only

For human use only

Single dose vial

Administer within 3 hours of reconstitution

Contains no preservative

Rx only

novo nordisk®

PACKAGE LABEL

Principal Display Panel 1 mg

NDC 0169-7201-01

List: 720101 1 mg
NovoSeven® RT
Coagulation Factor VIIa (Recombinant)

Room Temperature Stable

For bolus intravenous administration. For human use only.

Single-dose vial. Administer within 3 hours of reconstitution. Discard unused portion.

Contains no preservative.

Rx Only

Includes MixPro®
A vial adapter and pre-filled diluent syringe

PACKAGE LABEL

Principal Display Panel 2 mg

NDC 0169-7202-01

List: 720201 2 mg
NovoSeven® RT
Coagulation Factor VIIa (Recombinant)

Room Temperature Stable

For bolus intravenous administration. For human use only.

Single-dose vial. Administer within 3 hours of reconstitution. Discard unused portion.

Contains no preservative.

Rx Only

Includes MixPro®

A vial adapter and pre-filled diluent syringe

PACKAGE LABEL

Principal Display Panel 5 mg

NDC 0169-7205-01

List: 720501 5 mg
NovoSeven® RT
Coagulation Factor VIIa (Recombinant)

Room Temperature Stable

For bolus intravenous administration. For human use only.

Single-dose vial. Administer within 3 hours of reconstitution. Discard unused portion.

Contains no preservative.

Rx Only

Includes MixPro®

A vial adapter and pre-filled diluent syringe

PACKAGE LABEL

Principal Display Panel 8 mg

NDC 0169-7208-01

List: 720801 8 mg
NovoSeven® RT
Coagulation Factor VIIa (Recombinant)

Room Temperature Stable

For bolus intravenous administration. For human use only.

Single-dose vial. Administer within 3 hours of reconstitution. Discard unused portion.

Contains no preservative.

Rx Only

Includes MixPro®

A vial adapter and pre-filled diluent syringe

Principal Display Panel 1 mL Histidine Label

Principal Display Panel 2 mL Histidine Label

PACKAGE LABEL

Principal Display Panel 5 mL Histidine

PACKAGE LABEL

Principal Display Panel 1 mg. Vial

PACKAGE LABEL

Principal Display Panel 2 mg. Vial

PACKAGE LABEL

Principal Display Panel 5 mg. Vial

PACKAGE LABEL

Principal Display Panel 8 mg. Vial